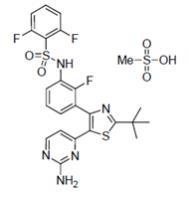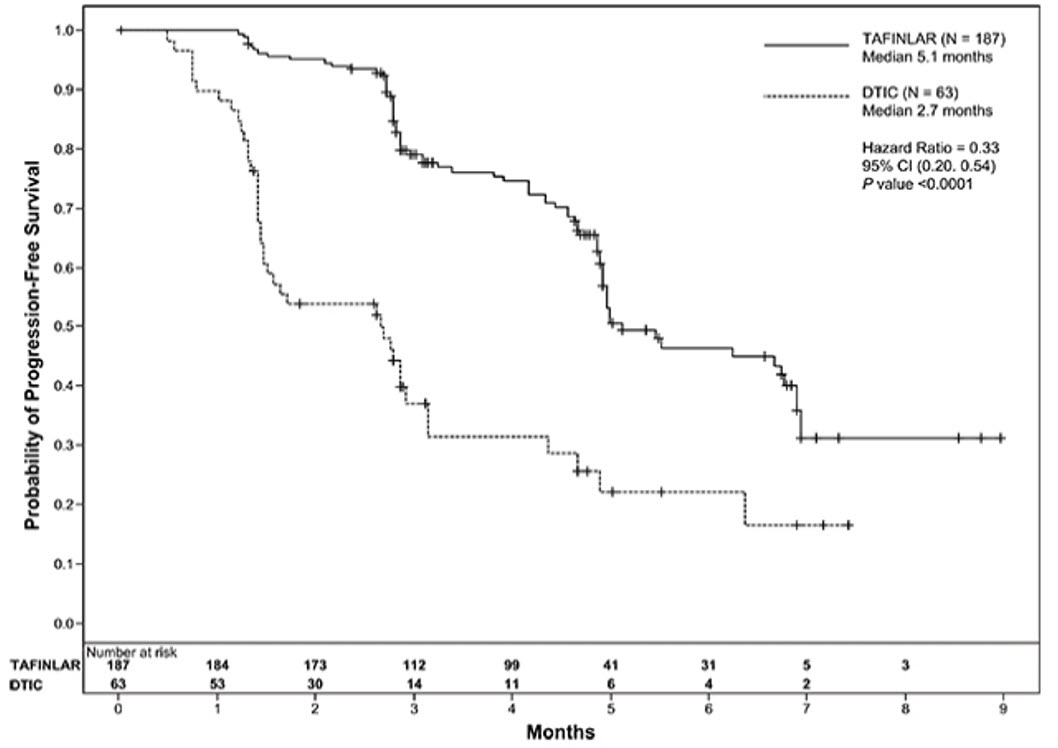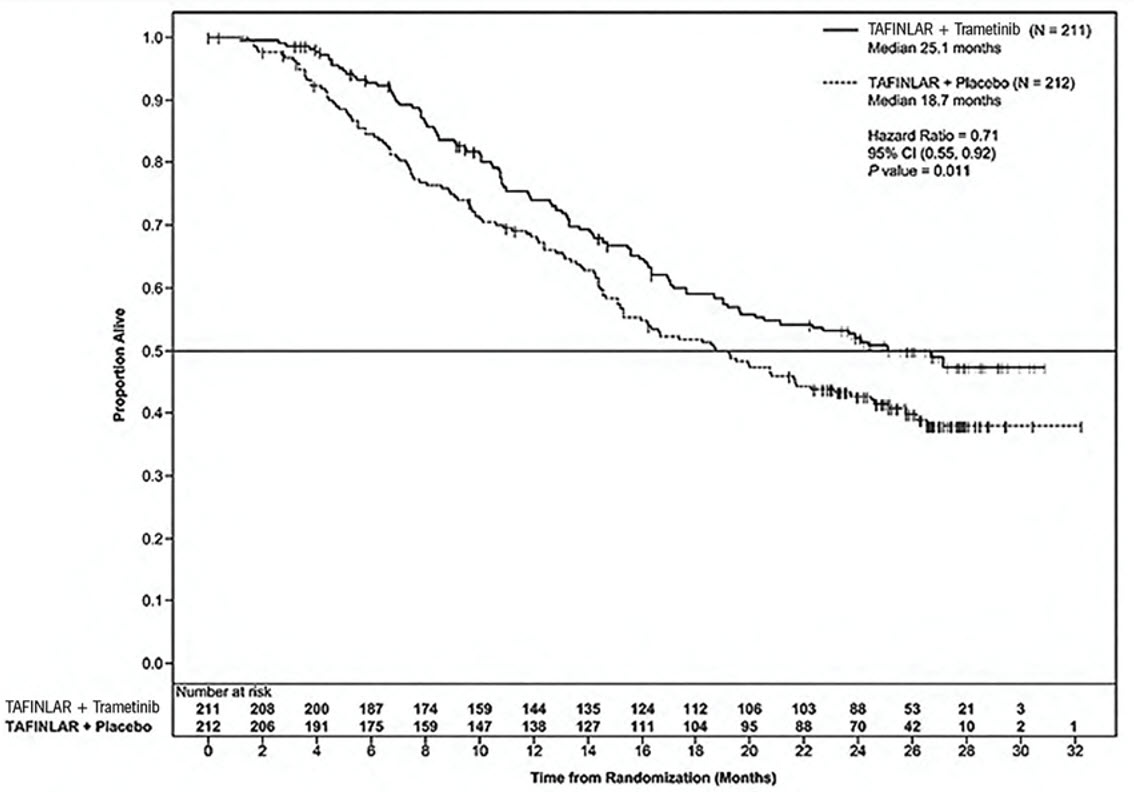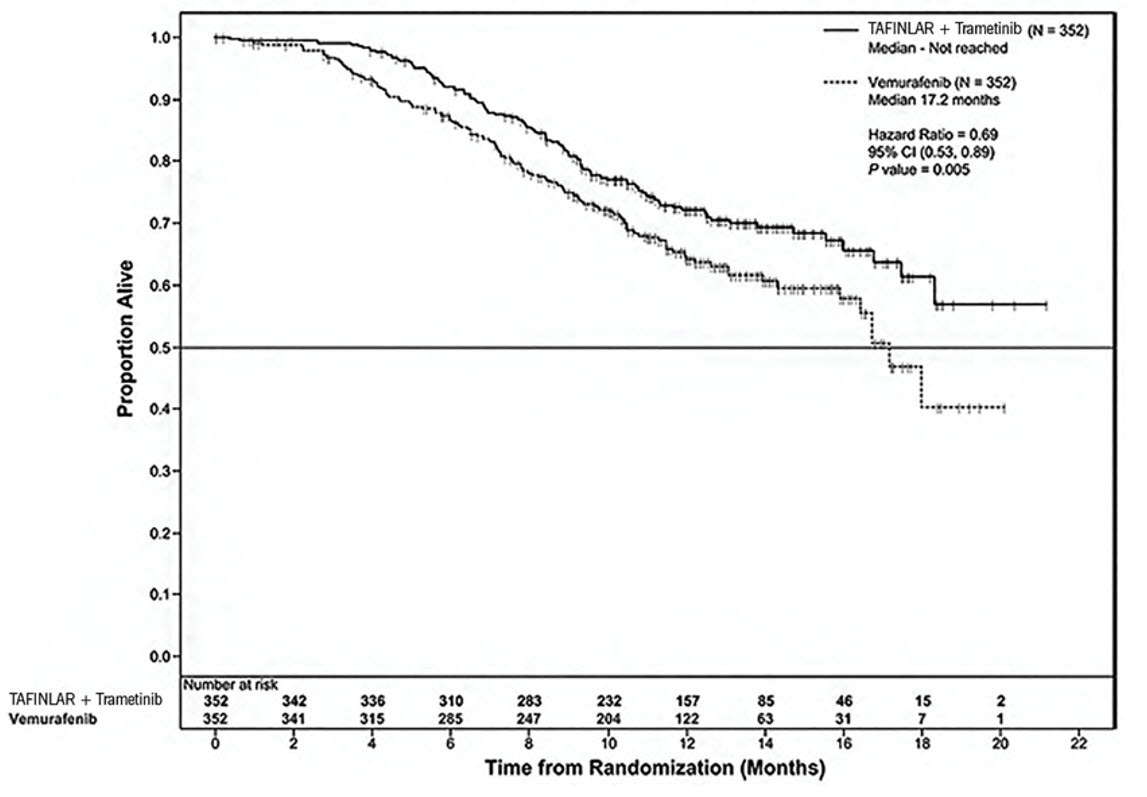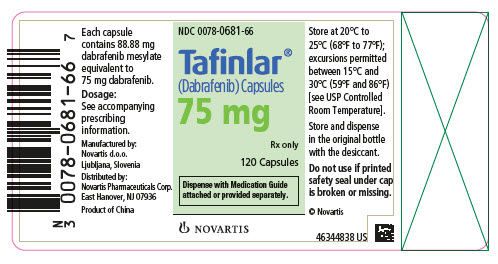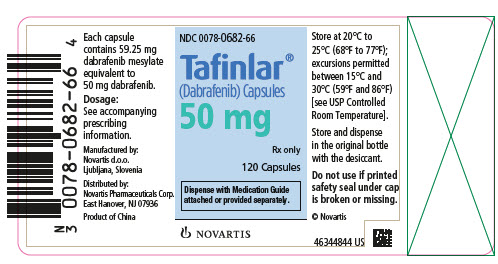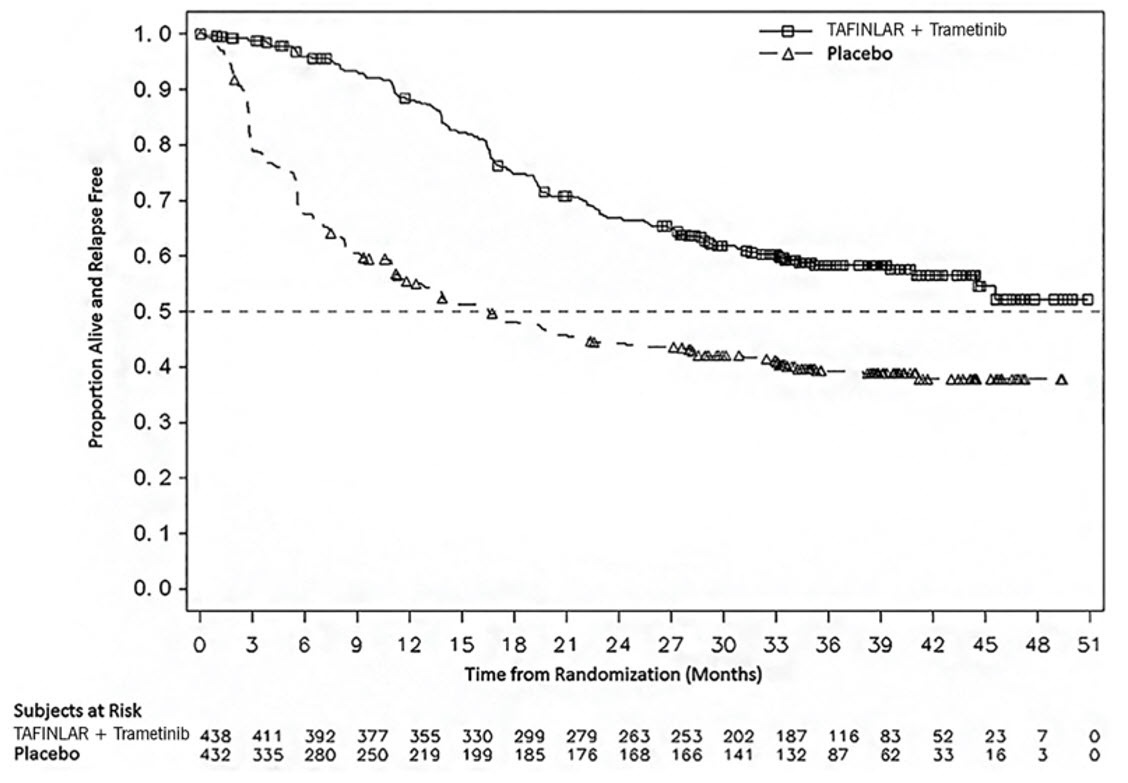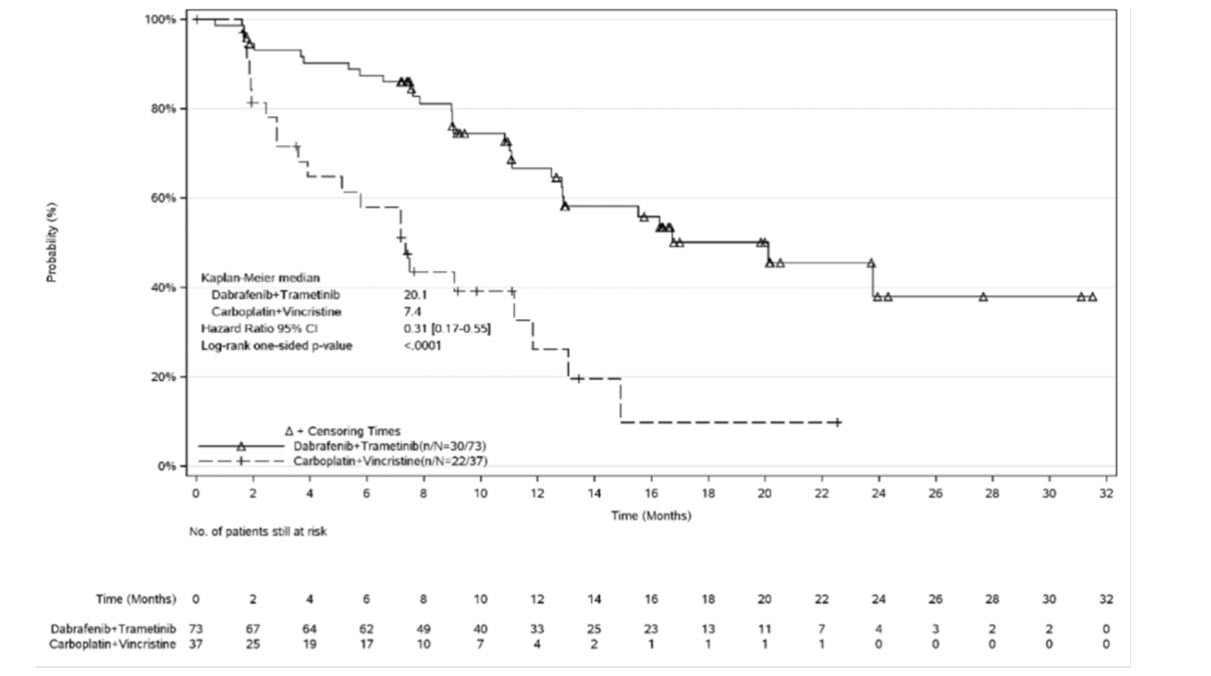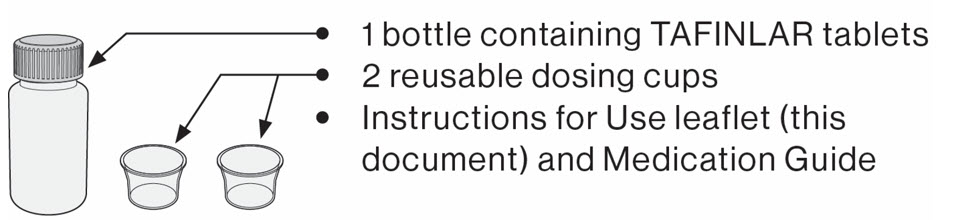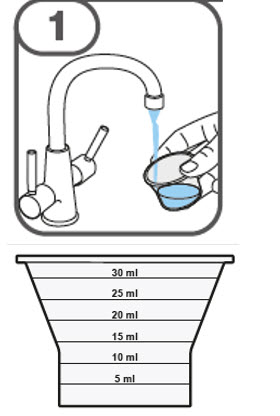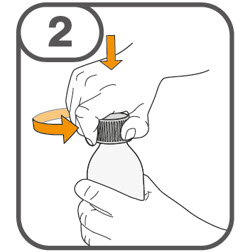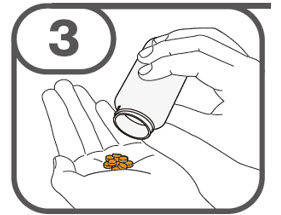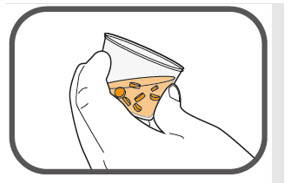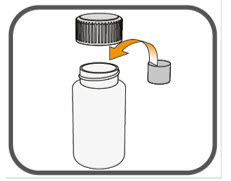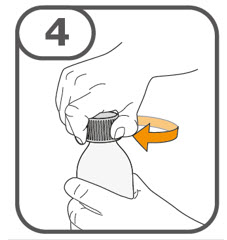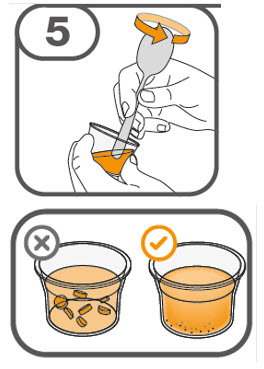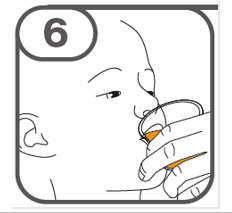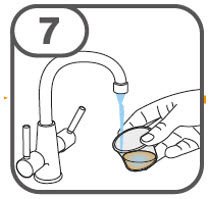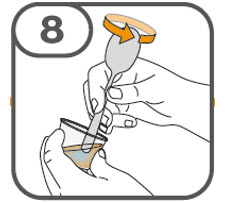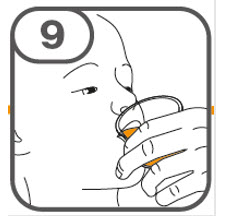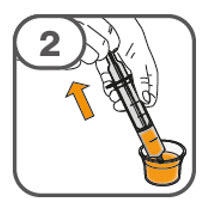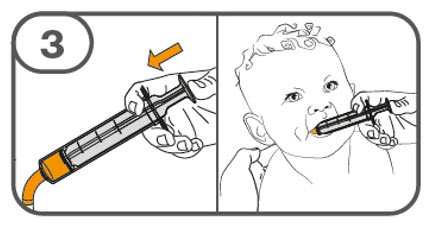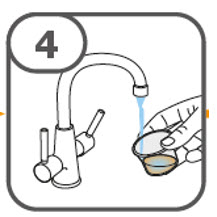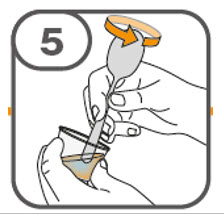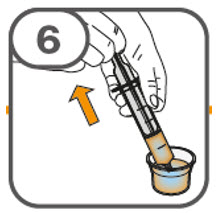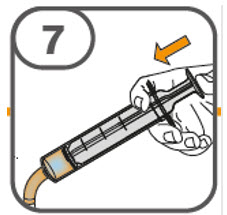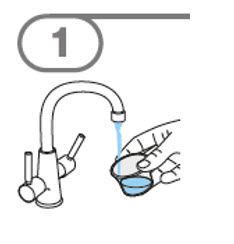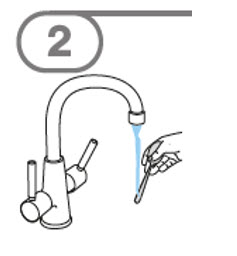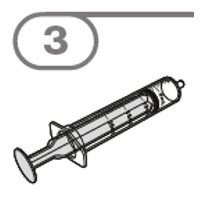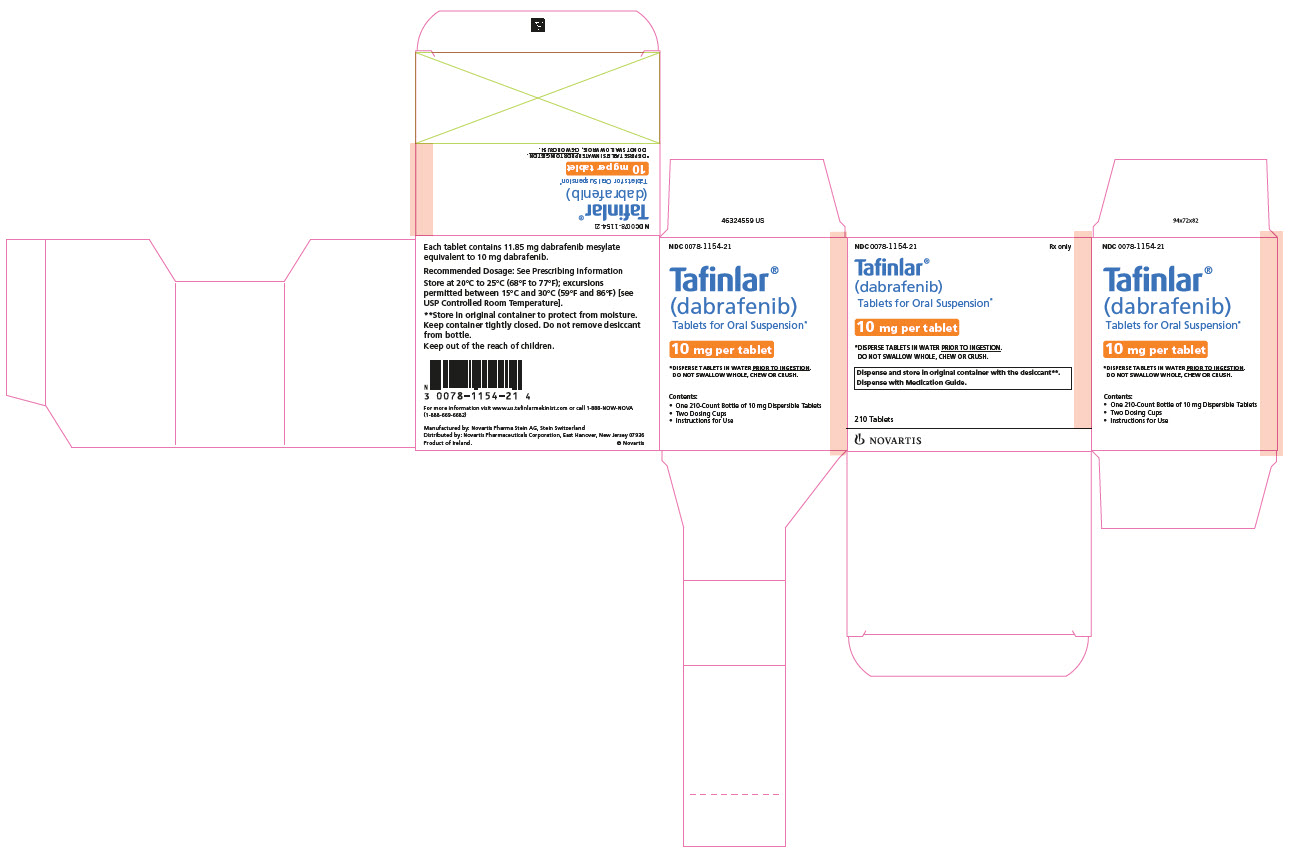 DRUG LABEL: Tafinlar
NDC: 0078-0682 | Form: CAPSULE
Manufacturer: Novartis Pharmaceuticals Corporation
Category: prescription | Type: HUMAN PRESCRIPTION DRUG LABEL
Date: 20250407

ACTIVE INGREDIENTS: DABRAFENIB MESYLATE 50 mg/1 1
INACTIVE INGREDIENTS: SILICON DIOXIDE; MAGNESIUM STEARATE; CELLULOSE, MICROCRYSTALLINE; HYPROMELLOSES; FERRIC OXIDE RED; TITANIUM DIOXIDE

HIGHLIGHTS OF PRESCRIBING INFORMATION

These highlights do not include all the information needed to use TAFINLAR safely and effectively. See full prescribing information for TAFINLAR.
TAFINLAR® (dabrafenib) capsules, for oral use
TAFINLAR® (dabrafenib) tablets for oral suspension
Initial U.S. Approval: 2013

RECENT MAJOR CHANGES

Indications and Usage, BRAF V600E Mutation-Positive Locally Advanced or Metastatic Anaplastic Thyroid Cancer (1.5) | 1/2025
Dosage and Administration, Patient Selection (2.1) | 1/2025
Dosage and Administration, Administration (2.3) | 3/2025
Warnings and Precautions, Uveitis (5.5) | 4/2025

1 INDICATIONS AND USAGE

TAFINLAR is a kinase inhibitor indicated as a single agent for the treatment of patients with unresectable or metastatic melanoma with BRAF V600E mutation as detected by an FDA-approved test. (1.1, 2.1)

TAFINLAR is indicated, in combination with trametinib, for:

- the treatment of patients with unresectable or metastatic melanoma with BRAF V600E or V600K mutations as detected by an FDA-approved test. (1.2, 2.1)
- the adjuvant treatment of patients with melanoma with BRAF V600E or V600K mutations, as detected by an FDA-approved test, and involvement of lymph node(s), following complete resection. (1.3, 2.1)
- the treatment of patients with metastatic non-small cell lung cancer (NSCLC) with BRAF V600E mutation as detected by an FDA-approved test. (1.4, 2.1)
- the treatment of patients with locally advanced or metastatic anaplastic thyroid cancer (ATC) with BRAF V600E mutation, as detected by an FDA-approved test, and with no satisfactory locoregional treatment options. (1.5, 2.1)
- the treatment of adult and pediatric patients 1 year of age and older with unresectable or metastatic solid tumors with BRAF V600E mutation who have progressed following prior treatment and have no satisfactory alternative treatment options. This indication is approved under accelerated approval based on overall response rate (ORR) and duration of response (DoR). Continued approval for this indication may be contingent upon verification and description of clinical benefit in a confirmatory trial(s). (1.6, 2.1)
- the treatment of pediatric patients 1 year of age and older with low-grade glioma (LGG) with a BRAF V600E mutation who require systemic therapy. (1.7, 2.1)

Limitations of Use: TAFINLAR is not indicated for treatment of patients with colorectal cancer because of known intrinsic resistance to BRAF inhibition. (1.8, 12.1) TAFINLAR is not indicated for treatment of patients with wild-type BRAF solid tumors. (5.2)

2 DOSAGE AND ADMINISTRATION

- The recommended dosage of TAFINLAR in adult patients is 150 mg (two 75 mg capsules) orally twice daily. The recommended dosage for TAFINLAR in pediatric patients is based on body weight. Take TAFINLAR at least 1 hour before or 2 hours after a meal. (2)

3 DOSAGE FORMS AND STRENGTHS

TAFINLAR Capsules: 50 mg, 75 mg (3)

TAFINLAR Tablets for Oral Suspension: 10 mg (3)

4 CONTRAINDICATIONS

None. (4)

5 WARNINGS AND PRECAUTIONS

- New Primary Malignancies, Cutaneous and Non-Cutaneous: Can occur when TAFINLAR is administered as a single agent or with trametinib. Monitor patients for new malignancies prior to, or while on therapy, and following discontinuation of treatment. (5.1, 2.4)
- Tumor Promotion in BRAF Wild-type Tumors: Increased cell proliferation can occur with BRAF inhibitors. (5.2, 2.1)
- Hemorrhage: Major hemorrhagic events can occur in patients receiving TAFINLAR with trametinib. Monitor for signs and symptoms of bleeding. (5.3)
- Cardiomyopathy: Assess left ventricular ejection fraction (LVEF) before treatment with TAFINLAR and trametinib, after one month of treatment, then every 2 to 3 months thereafter. (5.4, 2.4)
- Uveitis: Perform ophthalmological evaluation for any visual disturbances. (5.5, 2.4)
- Serious Febrile Reactions: Incidence and severity of pyrexia are increased with TAFINLAR and trametinib. (5.6, 2.4)
- Serious Skin Toxicities: Monitor for skin toxicities. Discontinue for intolerable Grade 2 or for Grade 3 or 4 rash not improving within 3 weeks despite interruption of TAFINLAR. Permanently discontinue for severe cutaneous adverse reactions (SCARs). (5.7, 2.4)
- Hyperglycemia: Monitor serum glucose levels in patients with preexisting diabetes or hyperglycemia. (5.8)
- Glucose-6-phosphate Dehydrogenase Deficiency (G6PD): Closely monitor for hemolytic anemia. (5.9)
- Hemophagocytic Lymphohistiocytosis (HLH): Interrupt treatment for suspected HLH. Discontinue treatment if HLH is confirmed. (5.11)
- Embryo-Fetal Toxicity: Can cause fetal harm. Advise females of reproductive potential of potential risk to a fetus and to use an effective non-hormonal method of contraception. (5.12, 8.1, 8.3)

6 ADVERSE REACTIONS

Most common adverse reactions (≥ 20%) for TAFINLAR as a single agent are hyperkeratosis, headache, pyrexia, arthralgia, papilloma, alopecia, and palmar-plantar erythrodysesthesia syndrome. (6.1)

Most common adverse reactions (≥ 20%) for TAFINLAR in combination with trametinib include:

- Unresectable or metastatic melanoma: pyrexia, rash, chills, headache, arthralgia, and cough. (6.1)
- Adjuvant treatment of melanoma: pyrexia, fatigue, nausea, headache, rash, chills, diarrhea, vomiting, arthralgia, and myalgia. (6.1)
- NSCLC: pyrexia, fatigue, nausea, vomiting, diarrhea, dry skin, decreased appetite, edema, rash, chills, hemorrhage, cough, and dyspnea. (6.1)
- Adult patients with solid tumors: pyrexia, fatigue, nausea, rash, chills, headache, hemorrhage, cough, vomiting, constipation, diarrhea, myalgia, arthralgia, and edema. (6.1)
- Pediatric patients with solid tumors: pyrexia, rash, vomiting, fatigue, dry skin, cough, diarrhea, dermatitis acneiform, headache, abdominal pain, nausea, hemorrhage, constipation, and paronychia. (6.1)
- Pediatric patients with LGG: pyrexia, rash, headache, vomiting, musculoskeletal pain, fatigue, diarrhea, dry skin, nausea, hemorrhage, abdominal pain, and dermatitis acneiform. (6.1)

To report SUSPECTED ADVERSE REACTIONS, contact Novartis Pharmaceuticals Corporation at 1-888-669-6682 or FDA at 1-800-FDA-1088 or www.fda.gov/medwatch.

7 DRUG INTERACTIONS

- Avoid concurrent administration of strong inhibitors of CYP3A4 or CYP2C8. (7.1)
- Concomitant use with agents that are sensitive substrates of CYP3A4, CYP2C8, CYP2C9, CYP2C19, or CYP2B6 may result in loss of efficacy of these agents. (7.2)

8 USE IN SPECIFIC POPULATIONS

- Lactation: Do not breastfeed. (8.2)
- Females and Males of Reproductive Potential: May impair fertility. (8.3)

FULL PRESCRIBING INFORMATION

1 INDICATIONS AND USAGE

1.1 BRAF V600E Mutation-Positive Unresectable or Metastatic Melanoma

TAFINLAR® is indicated as a single agent for the treatment of patients with unresectable or metastatic melanoma with BRAF V600E mutation as detected by an FDA-approved test.

1.2 BRAF V600E or V600K Mutation-Positive Unresectable or Metastatic Melanoma

TAFINLAR is indicated, in combination with trametinib, for the treatment of patients with unresectable or metastatic melanoma with BRAF V600E or V600K mutations, as detected by an FDA-approved test [see Dosage and Administration (2.1)].

1.3 Adjuvant Treatment of BRAF V600E or V600K Mutation-Positive Melanoma

TAFINLAR is indicated, in combination with trametinib, for the adjuvant treatment of patients with melanoma with BRAF V600E or V600K mutations, as detected by an FDA-approved test, and involvement of lymph node(s), following complete resection [see Dosage and Administration (2.1)].

1.4 BRAF V600E Mutation-Positive Metastatic NSCLC

TAFINLAR is indicated, in combination with trametinib, for the treatment of patients with metastatic non-small cell lung cancer (NSCLC) with BRAF V600E mutation as detected by an FDA-approved test [see Dosage and Administration (2.1)].

1.5 BRAF V600E Mutation-Positive Locally Advanced or Metastatic Anaplastic Thyroid Cancer

TAFINLAR is indicated, in combination with trametinib, for the treatment of patients with locally advanced or metastatic anaplastic thyroid cancer (ATC) with BRAF V600E mutation, as detected by an FDA-approved test, and with no satisfactory locoregional treatment options [see Dosage and Administration (2.1)].

1.6 BRAF V600E Mutation-Positive Unresectable or Metastatic Solid Tumors

TAFINLAR is indicated, in combination with trametinib, for the treatment of adult and pediatric patients 1 year of age and older with unresectable or metastatic solid tumors with BRAF V600E mutation who have progressed following prior treatment and have no satisfactory alternative treatment options [see Dosage and Administration (2.1)]. This indication is approved under accelerated approval based on overall response rate (ORR) and duration of response (DoR) [see Clinical Studies (14.6)]. Continued approval for this indication may be contingent upon verification and description of clinical benefit in a confirmatory trial(s).

1.7 BRAF V600E Mutation-Positive Low-Grade Glioma

TAFINLAR is indicated, in combination with trametinib, for the treatment of pediatric patients 1 year of age and older with low-grade glioma (LGG) with a BRAF V600E mutation who require systemic therapy [see Dosage and Administration (2.1)].

1.8 Limitations of Use

- TAFINLAR is not indicated for treatment of patients with colorectal cancer because of known intrinsic resistance to BRAF inhibition [see Indications and Usage (1.6), Clinical Pharmacology (12.1)].
- TAFINLAR is not indicated for treatment of patients with wild-type BRAF solid tumors [see Warnings and Precautions (5.2)].

2 DOSAGE AND ADMINISTRATION

2.1 Patient Selection

Melanoma

- Confirm the presence of BRAF V600E mutation in tumor specimens prior to initiation of treatment with TAFINLAR as a single agent [see Warnings and Precautions (5.2), Clinical Studies (14.1)].
- Confirm the presence of BRAF V600E or V600K mutation in tumor specimens prior to initiation of treatment with TAFINLAR and trametinib [see Warnings and Precautions (5.2), Clinical Studies (14.2, 14.3)].
- Information on FDA-approved tests for the detection of BRAF V600 mutations in melanoma is available at: http://www.fda.gov/CompanionDiagnostics.

NSCLC

- Confirm the presence of BRAF V600E mutation in tumor specimens prior to initiation of treatment with TAFINLAR and trametinib [see Clinical Studies (14.4)].
- Information on FDA-approved tests for the detection of BRAF V600E mutations in NSCLC is available at: http://www.fda.gov/CompanionDiagnostics.

ATC

- Confirm the presence of BRAF V600E mutation in tumor specimens prior to initiation of treatment with TAFINLAR and trametinib [see Clinical Studies (14.5)].
- Information on FDA-approved tests for the detection of BRAF V600E mutations in ATC is available at: http://www.fda.gov/CompanionDiagnostics.

Solid Tumors

- Confirm the presence of BRAF V600E mutation in tumor specimens prior to initiation of treatment with TAFINLAR and trametinib [see Clinical Studies (14.6)]. An FDA-approved test for the detection of BRAF V600E mutation in solid tumors other than melanoma and NSCLC is not currently available.

Low-Grade Glioma

- Confirm the presence of BRAF V600E mutation in tumor specimens prior to initiation of treatment with TAFINLAR and trametinib [see Clinical Studies (14.7)]. An FDA-approved test for the detection of BRAF V600E mutation in LGG is not currently available.

2.2 Recommended Dosage

TAFINLAR Capsules

Adult Patients

The recommended dosage for TAFINLAR capsules in adult patients is 150 mg taken orally twice daily [see Dosage and Administration (2.3)].

Pediatric Patients

The recommended dosage for TAFINLAR capsules in pediatric patients who weigh at least 26 kg is based on body weight (Table 1) [see Dosage and Administration (2.3)]. A recommended dosage of TAFINLAR capsules has not been established in patients who weigh less than 26 kg.

Table 1. Recommended Dosage for TAFINLAR Capsules in Pediatric Patients (Weight-based)
Body Weight | Recommended Dosage
26 to 37 kg | 75 mg orally twice daily
38 to 50 kg | 100 mg orally twice daily
51 kg or greater | 150 mg orally twice daily

TAFINLAR Tablets for Oral Suspension

Adult and Pediatric Patients

The recommended dosage for TAFINLAR tablets for oral suspension for adult and pediatric patients is based on body weight (Table 2) [see Dosage and Administration (2.3)].

Table 2. Recommended Dosage for TAFINLAR Tablets for Oral Suspension in Adult and Pediatric Patients (Weight-based)
Body Weight | Recommended Dosage
8 to 9 kg | 20 mg twice daily
10 to 13 kg | 30 mg twice daily
14 to 17 kg | 40 mg twice daily
18 to 21 kg | 50 mg twice daily
22 to 25 kg | 60 mg twice daily
26 to 29 kg | 70 mg twice daily
30 to 33 kg | 80 mg twice daily
34 to 37 kg | 90 mg twice daily
38 to 41 kg | 100 mg twice daily
42 to 45 kg | 110 mg twice daily
46 to 50 kg | 130 mg twice daily
≥ 51 kg | 150 mg twice daily

Duration of Treatment

- The recommended duration of treatment for patients with unresectable or metastatic melanoma or solid tumors, metastatic NSCLC, or locally advanced or metastatic anaplastic thyroid cancer is until disease progression or unacceptable toxicity.
- The recommended duration of treatment in the adjuvant melanoma setting is until disease recurrence or unacceptable toxicity for up to 1 year.
- The recommended duration of treatment for pediatric patients with LGG is until disease progression or until unacceptable toxicity.

Combination Therapy with Trametinib

Refer to the trametinib prescribing information for recommended trametinib dosing information.

2.3 Administration

- Take TAFINLAR at the same time each day, approximately 12 hours apart.
- Do not take a missed dose of TAFINLAR within 6 hours of the next dose of TAFINLAR.
- If vomiting occurs after TAFINLAR administration, do not take an additional dose. Take the next dose at its scheduled time.

TAFINLAR Capsules

- Take TAFINLAR capsules on an empty stomach (at least 1 hour before or 2 hours after a meal) [see Clinical Pharmacology (12.3)].
- Do not open, crush, or break TAFINLAR capsules.

TAFINLAR Tablets for Oral Suspension

- Prior to use of the oral suspension, instruct caregivers (and if appropriate, patients) on proper dosing and administration of TAFINLAR tablets for oral suspension.
- Take the oral suspension on an empty stomach (at least 1 hour before or 2 hours after a meal). Breastfeeding and/or baby formula may be given on demand if a pediatric patient is unable to tolerate the fasting conditions [see Clinical Pharmacology (12.3)].
- Do not swallow whole, chew or crush TAFINLAR tablets for oral suspension.

Preparation and Administration

- Prepare the oral suspension with approximately 5 mL of water for 1 to 4 tablets, and approximately 10 mL of water for 5 to 15 tablets in the provided dosing cup.
- Gently stir the water and prescribed number of tablets with the handle of a teaspoon until the tablets are fully dissolved. It may take at least 3 minutes to fully dissolve the tablets. Once the tablets are dissolved, the oral suspension will be cloudy white.
- Administer the oral suspension immediately after preparation from a dosing cup, oral syringe or feeding tube (10 French gauge or larger for 1 to 3 tablets; 12 French gauge or larger for 4 to 15 tablets).
- Discard the oral suspension if not administered within 30 minutes after preparation.

2.4 Dosage Modifications for Adverse Reactions

Dose reductions for adverse reactions associated with TAFINLAR are presented in Tables 3 and 4.

Table 3. Recommended Dosage Reductions for TAFINLAR Capsules for Adverse Reactions
Recommended Dosage | 75 mg orally twice daily | 100 mg orally twice daily | 150 mg orally twice daily
First dose reduction | 50 mg orally twice daily | 75 mg orally twice daily | 100 mg orally twice daily
Second dose reduction | N/A | 50 mg orally twice daily | 75 mg orally twice daily
Third dose reduction | N/A | N/A | 50 mg orally twice daily
Subsequent modification | Permanently discontinue if unable to tolerate TAFINLAR capsules 50 mg orally twice daily.

Table 4. Recommended Dosage Reductions for TAFINLAR Tablets for Oral Suspension for Adverse Reactions
Body Weight (Recommended dosage) | First Dose Reduction | Second Dose Reduction | Third Dose Reduction
 | Tablets for oral suspension twice daily
8 to 9 kg (20 mg twice daily) | 10 mg twice daily | N/A | N/A
10 to 13 kg (30 mg twice daily) | 20 mg twice daily | 10 mg twice daily | N/A
14 to 17 kg (40 mg twice daily) | 30 mg twice daily | 20 mg twice daily | 10 mg twice daily
18 to 21 kg (50 mg twice daily) | 30 mg twice daily | 20 mg twice daily | 10 mg twice daily
22 to 25 kg (60 mg twice daily) | 40 mg twice daily | 30 mg twice daily | 20 mg twice daily
26 to 29 kg (70 mg twice daily) | 50 mg twice daily | 40 mg twice daily | 20 mg twice daily
30 to 33 kg (80 mg twice daily) | 50 mg twice daily | 40 mg twice daily | 30 mg twice daily
34 to 37 kg (90 mg twice daily) | 60 mg twice daily | 50 mg twice daily | 30 mg twice daily
38 to 41 kg (100 mg twice daily) | 70 mg twice daily | 50 mg twice daily | 30 mg twice daily
42 to 45 kg (110 mg twice daily) | 70 mg twice daily | 60 mg twice daily | 40 mg twice daily
46 to 50 kg (130 mg twice daily) | 90 mg twice daily | 70 mg twice daily | 40 mg twice daily
≥ 51 kg (150 mg twice daily) | 100 mg twice daily | 80 mg twice daily | 50 mg twice daily

Dosage modifications for adverse reactions associated with TAFINLAR are presented in Table 5.

Table 5. Recommended Dosage Modifications for TAFINLAR for Adverse Reactions
Severity of Adverse Reactiona | Dosage Modification for TAFINLARb
New Primary Malignancies [see Warnings and Precautions (5.1)]
Non-Cutaneous RAS Mutation-positive Malignancies | Permanently discontinue TAFINLAR.
Cardiomyopathy [see Warnings and Precautions (5.4)]
- Symptomatic cardiomyopathy - Absolute decrease in left ventricular ejection fraction (LVEF) of greater than 20% from baseline that is below the institutional lower limit of normal (LLN) | Withhold TAFINLAR until LVEF improves to at least the institutional LLN and absolute decrease to less than or equal to 10% compared to baseline, then resume TAFINLAR at same dose.
Uveitis [see Warnings and Precautions (5.5)]
- Uveitis, including iritis and iridocyclitis | For mild or moderate uveitis that does not respond to ocular therapy, or for severe uveitis, withhold TAFINLAR for up to 6 weeks.; - If improved to Grade 0-1, then resume TAFINLAR at same or lower dose. - If not improved, permanently discontinue TAFINLAR.
Febrile Reactions [see Warnings and Precautions (5.6)]
- Fever of 100.4°F to 104°F (or first symptoms in case of recurrence) | Withhold TAFINLAR until fever resolves, then resume TAFINLAR at same or lower dose.
- Fever higher than 104°F - Fever complicated by rigors, hypotension, dehydration, or renal failure | - Withhold TAFINLAR until febrile reactions resolve for at least 24 hours, then resume TAFINLAR at lower dose.; Or; - Permanently discontinue TAFINLAR.
Skin Toxicities [see Warnings and Precautions (5.7)]
- Intolerable Grade 2 - Grade 3 or 4 | Withhold TAFINLAR for up to 3 weeks.; - If improved, resume TAFINLAR at lower dose. - If not improved, permanently discontinue TAFINLAR.
- Severe cutaneous adverse reactions (SCARs) | Permanently discontinue TAFINLAR.
Other Adverse Reactionsc, including Hemorrhage [see Warnings and Precautions (5.3)]
- Intolerable Grade 2 - Any Grade 3 | Withhold TAFINLAR.; - If improved to Grade 0-1, resume TAFINLAR at lower dose. - If not improved, permanently discontinue TAFINLAR.
- First occurrence of any Grade 4 | - Withhold TAFINLAR until improves to Grade 0-1, then resume TAFINLAR at lower dose.; Or; - Permanently discontinue TAFINLAR.
- Recurrent Grade 4 | Permanently discontinue TAFINLAR.
a National Cancer Institute Common Terminology Criteria for Adverse Events (NCI CTCAE) version 4.0.
b See Tables 3 and 4 for recommended dose reductions of TAFINLAR.
c Dose modifications are not recommended for TAFINLAR when administered with trametinib for the following adverse reactions of trametinib: retinal vein occlusion (RVO), retinal pigment epithelial detachment (RPED), interstitial lung disease/pneumonitis, and uncomplicated venous thromboembolism. Dose modification of TAFINLAR is not required for new primary cutaneous malignancies.

Refer to the trametinib prescribing information for dose modifications for adverse reactions associated with trametinib.

3 DOSAGE FORMS AND STRENGTHS

TAFINLAR Capsules:

- 50 mg: Dark red capsule imprinted with ‘GS TEW’ and ‘50 mg’.
- 75 mg: Dark pink capsule imprinted with ‘GS LHF’ and ‘75 mg’.

TAFINLAR Tablets for Oral Suspension:

- 10 mg: White to slightly yellow, round, biconvex 6 mm tablet debossed with “D” on one side and “NVR” on the other, contains berry flavor.

4 CONTRAINDICATIONS

None.

5 WARNINGS AND PRECAUTIONS

5.1 New Primary Malignancies

Cutaneous Malignancies

TAFINLAR Monotherapy (Adult): In the pooled safety population [see Adverse Reactions (6.1)], cutaneous squamous cell carcinomas (cuSCC), and keratoacanthomas occurred in 11% and 4% of patients, respectively. Basal cell carcinoma and new primary melanoma occurred in 4% and 1% of patients, respectively.

TAFINLAR Administered with Trametinib (Adult): In the pooled safety population [see Adverse Reactions (6.1)], the incidence of cuSCC (including keratoacanthomas) occurred in 2% of patients. Basal cell carcinoma and new primary melanoma occurred in 3% and < 1% of patients, respectively.

TAFINLAR Administered with Trametinib (Pediatric): In the pooled safety population, new primary melanoma occurred in < 1% of patients.

Perform dermatologic evaluations prior to initiation of TAFINLAR, every 2 months while on therapy, and for up to 6 months following discontinuation of TAFINLAR.

Non-Cutaneous Malignancies

Based on its mechanism of action, TAFINLAR may promote the growth and development of malignancies with activation of RAS through mutation or other mechanisms [see Warnings and Precautions (5.2)].

In the pooled adult safety populations of TAFINLAR monotherapy and TAFINLAR administered with trametinib [see Adverse Reactions (6.1)], non-cutaneous malignancies occurred in 1% of patients.

Monitor patients receiving TAFINLAR for signs or symptoms of non-cutaneous malignancies. Permanently discontinue TAFINLAR for RAS mutation-positive non-cutaneous malignancies [see Dosage and Administration (2.4)].

5.2 Tumor Promotion in BRAF Wild-Type Tumors

In vitro experiments have demonstrated paradoxical activation of MAP-kinase signaling and increased cell proliferation in BRAF wild-type cells which are exposed to BRAF inhibitors. Confirm evidence of BRAF V600E or V600K mutation status prior to initiation of TAFINLAR as a single agent or in combination with trametinib [see Indications and Usage (1.6), Dosage and Administration (2.1)].

5.3 Hemorrhage

Hemorrhage, including major hemorrhage defined as symptomatic bleeding in a critical area or organ, can occur when TAFINLAR is administered with trametinib. Fatal cases have been reported.

TAFINLAR Administered with Trametinib (Adult): In the pooled safety population [see Adverse Reactions (6.1)], hemorrhagic events occurred in 17% of patients; gastrointestinal hemorrhage occurred in 3% of patients; intracranial hemorrhage occurred in 0.6% of patients; fatal hemorrhage occurred in 0.5% of patients. The fatal events were cerebral hemorrhage and brainstem hemorrhage.

TAFINLAR Administered with Trametinib (Pediatric): In the pooled safety population, hemorrhagic events occurred in 25% of patients; the most common type of bleeding was epistaxis (16%). Serious events of bleeding occurred in 3.6% of patients and included gastrointestinal hemorrhage (1.2%), cerebral hemorrhage (0.6%), uterine hemorrhage (0.6%), post-procedural hemorrhage (0.6%), and epistaxis (0.6%).

Permanently discontinue TAFINLAR for all Grade 4 hemorrhagic events and for any Grade 3 hemorrhagic events that do not improve. Withhold TAFINLAR for Grade 3 hemorrhagic events; if improved, resume TAFINLAR at the next lower dose level.

5.4 Cardiomyopathy

TAFINLAR Administered with Trametinib (Adult): In the pooled safety population [see Adverse Reactions (6.1)], cardiomyopathy, defined as a decrease in left ventricular ejection fraction (LVEF) ≥ 10% from baseline and below the institutional lower limit of normal (LLN), occurred in 6% of patients. Development of cardiomyopathy resulted in dose interruption or discontinuation of TAFINLAR in 3% and < 1% of patients, respectively. Cardiomyopathy resolved in 45 of 50 patients who received TAFINLAR administered with trametinib.

TAFINLAR Administered with Trametinib (Pediatric): In the pooled safety population, cardiomyopathy, defined as a decrease in LVEF ≥ 10% from baseline and below the institutional LLN, occurred in 9% of patients.

Assess LVEF by echocardiogram or multigated acquisition (MUGA) scan before initiation of TAFINLAR in combination with trametinib, one month after initiation, and then at 2- to 3-month intervals while on treatment. Withhold TAFINLAR for symptomatic cardiomyopathy or an absolute decrease in LVEF of greater than 20% from baseline that is below the institutional LLN. Resume TAFINLAR at the same dose level upon recovery of cardiac function to at least the institutional LLN for LVEF and absolute decrease to less than or equal to 10% compared to baseline [see Dosage and Administration (2.4)].

5.5 Uveitis

TAFINLAR Monotherapy (Adult): In the pooled safety population [see Adverse Reactions (6.1)], uveitis occurred in 1% of patients.

Cases of biocular panuveitis or biocular iridocyclitis have been reported in the post-marketing setting.

TAFINLAR Administered with Trametinib (Adult): In the pooled safety population [see Adverse Reactions (6.1)], uveitis occurred in 2% of patients.

TAFINLAR Administered with Trametinib (Pediatric): In the pooled safety population, uveitis occurred in 1.2% of patients.

Treatment employed in clinical trials included steroid and mydriatic ophthalmic drops. Monitor patients for visual signs and symptoms of uveitis (e.g., change in vision, photophobia, eye pain). If iritis is diagnosed, administer ocular therapy and continue TAFINLAR without dose modification. If severe uveitis (i.e., iridocyclitis) or if mild or moderate uveitis does not respond to ocular therapy, withhold TAFINLAR and treat as clinically indicated. Resume TAFINLAR at the same or lower dose if improves to Grade 0 or 1. Permanently discontinue TAFINLAR for persistent Grade 2 or greater uveitis of > 6 weeks [see Dosage and Administration (2.4)].

5.6 Serious Febrile Reactions

Serious febrile reactions and fever of any severity complicated by hypotension, rigors or chills, dehydration, or renal failure, can occur with TAFINLAR.

The incidence and severity of pyrexia are increased when TAFINLAR is administered with trametinib compared with TAFINLAR as a single agent [see Adverse Reactions (6.1)].

TAFINLAR Monotherapy (Adult): In the pooled safety population [see Adverse Reactions (6.1)], fever (serious and non-serious) occurred in 30% of patients. Approximately 13% of these patients experienced 3 or more discrete episodes. Serious febrile reactions and fever of any severity complicated by hypotension, rigors or chills occurred in 6% of patients.

TAFINLAR Administered with Trametinib (Adult): In the pooled safety population [see Adverse Reactions (6.1)], fever occurred in 58% of patients. Serious febrile reactions and fever of any severity complicated by hypotension, rigors or chills, dehydration or renal failure occurred in 5% of patients. Fever was complicated by hypotension in 4%, dehydration in 3%, syncope in 2%, renal failure in 1%, and severe chills/rigors in < 1% of patients.

TAFINLAR Administered with Trametinib (Pediatric): In the pooled safety population [see Adverse Reactions (6.1)], pyrexia occurred in 66% of patients.

Withhold TAFINLAR when used as monotherapy, and both TAFINLAR and trametinib when used in combination, if the patient’s temperature is ≥ 100.4°F. In case of recurrence, therapy can also be interrupted at the first symptom of pyrexia [see Adverse Reactions (6.1)]. Fever may be complicated by hypotension, rigors or chills, dehydration, or renal failure. Evaluate for signs and symptoms of infection and monitor serum creatinine and other evidence of renal function during and following severe pyrexia. If appropriate, TAFINLAR, or both TAFINLAR and trametinib when used in combination, may be restarted if the patient has recovered from the febrile reaction for at least 24 hours, either at the same or lower dose [see Dosage and Administration (2.4)]. Administer antipyretics as secondary prophylaxis when resuming TAFINLAR if patient had a prior episode of severe febrile reaction or fever associated with complications. Administer corticosteroids (e.g., prednisone 10 mg daily) for at least 5 days for second or subsequent pyrexia if temperature does not return to baseline within 3 days of onset of pyrexia, or for pyrexia associated with complications, such as dehydration, hypotension, renal failure, or severe chills/rigors, and there is no evidence of active infection.

5.7 Serious Skin Toxicities

Severe cutaneous adverse reactions (SCARs), including Stevens-Johnson syndrome (SJS) and drug reaction with eosinophilia and systemic symptoms (DRESS), which can be life-threatening or fatal, have been reported during treatment with TAFINLAR administered with trametinib [see Adverse Reactions (6.2)].

TAFINLAR Administered with Trametinib (Adult): In the pooled safety population [see Adverse Reactions (6.1)], other serious skin toxicity occurred in < 1% of patients.

TAFINLAR Administered with Trametinib (Pediatric): In the pooled safety population, serious adverse events of skin and subcutaneous tissue disorders occurred in 1.8% of patients.

Monitor for new or worsening serious skin reactions. Permanently discontinue TAFINLAR for SCARs [see Dosage and Administration (2.4)]. For other skin toxicities, withhold TAFINLAR for intolerable or severe skin toxicity. Resume TAFINLAR at a lower dose in patients with improvement or recovery from skin toxicity within 3 weeks. Permanently discontinue TAFINLAR if skin toxicity has not improved within 3 weeks [see Dosage and Administration (2.4)].

5.8 Hyperglycemia

TAFINLAR Monotherapy (Adult): In the pooled safety population [see Adverse Reactions (6.1)], 14% of patients with a history of diabetes that received TAFINLAR required more intensive hypoglycemic therapy. Grade 3 and Grade 4 hyperglycemia occurred in 3% of patients.

TAFINLAR Administered with Trametinib (Adult): In the pooled safety population [see Adverse Reactions (6.1)], 15% of patients with a history of diabetes who had received TAFINLAR with trametinib required more intensive hypoglycemic therapy. Grade 3 and Grade 4 hyperglycemia occurred in 2% of patients.

TAFINLAR Administered with Trametinib (Pediatric): In the pooled safety population, Grade 3 and Grade 4 hyperglycemia events occurred in < 1% of patients.

Monitor serum glucose levels upon initiation and as clinically appropriate when TAFINLAR is administered in patients with preexisting diabetes or hyperglycemia. Initiate or optimize anti-hyperglycemic medications as clinically indicated.

5.9 Glucose-6-Phosphate Dehydrogenase Deficiency

TAFINLAR, which contains a sulfonamide moiety, confers a potential risk of hemolytic anemia in patients with glucose-6-phosphate dehydrogenase (G6PD) deficiency. Monitor patients with G6PD deficiency for signs of hemolytic anemia while taking TAFINLAR.

5.10 Risks Associated with Combination Treatment

TAFINLAR is indicated for use in combination with trametinib. Review the prescribing information for trametinib for information on the serious risks of trametinib prior to initiation of TAFINLAR with trametinib.

5.11 Hemophagocytic Lymphohistiocytosis

Hemophagocytic lymphohistiocytosis (HLH) has been observed in the post-marketing setting when TAFINLAR was administered with trametinib. If HLH is suspected, interrupt treatment. If HLH is confirmed, discontinue treatment and initiate appropriate management of HLH.

5.12 Embryo-Fetal Toxicity

Based on findings from animal studies and its mechanism of action, TAFINLAR can cause fetal harm when administered to a pregnant woman. Dabrafenib was teratogenic and embryotoxic in rats at doses three times greater than the human exposure at the recommended adult clinical dose. Advise pregnant women of the potential risk to a fetus. Advise female patients of reproductive potential to use effective non-hormonal contraception, since TAFINLAR can render hormonal contraceptives ineffective, during treatment with TAFINLAR and for 2 weeks after the last dose [see Drug Interactions (7.2), Use in Specific Populations (8.1, 8.3)].

6 ADVERSE REACTIONS

The following clinically significant adverse reactions are described elsewhere in the labeling:

- New Primary Malignancies [see Warnings and Precautions (5.1)]
- Tumor Promotion in BRAF Wild-Type Tumors [see Warnings and Precautions (5.2)]
- Hemorrhage [see Warnings and Precautions (5.3)]
- Cardiomyopathy [see Warnings and Precautions (5.4)]
- Uveitis [see Warnings and Precautions (5.5)]
- Serious Febrile Reactions [see Warnings and Precautions (5.6)]
- Serious Skin Toxicities [see Warnings and Precautions (5.7)]
- Hyperglycemia [see Warnings and Precautions (5.8)]
- Glucose-6-Phosphate Dehydrogenase Deficiency [see Warnings and Precautions (5.9)]
- Hemophagocytic Lymphohistiocytosis [see Warnings and Precautions (5.11)]

There are additional adverse reactions associated with trametinib. Refer to the trametinib prescribing information for additional information.

6.1 Clinical Trials Experience

Because clinical trials are conducted under widely varying conditions, adverse reaction rates observed in the clinical trials of a drug cannot be directly compared to rates in the clinical trials of another drug and may not reflect the rates observed in practice.

Adult Safety Pools

The pooled safety population described in the WARNINGS AND PRECAUTIONS reflects exposure to TAFINLAR 150 mg orally, twice daily as a single agent in 586 patients with various solid tumors, including BRAF V600 mutation-positive unresectable or metastatic melanoma, enrolled in BREAK-2, BREAK-3, BREAK-MB, BRF113220, and BRF112680. Among these 586 patients who received TAFINLAR as a single agent, 46% were exposed for 6 months or longer and 15% were exposed for greater than one year.

The pooled safety population described in the WARNINGS AND PRECAUTIONS reflects exposure to TAFINLAR 150 mg orally, twice daily, administered in combination with trametinib 2 mg orally, once daily, in 1087 patients enrolled in COMBI-d, COMBI-v, COMBI-AD, and BRF113928 with unresectable or metastatic melanoma, adjuvant melanoma, or NSCLC. Among these 1087 patients who received TAFINLAR administered with trametinib, 70% were exposed for 6 months or longer and 21% were exposed for greater than one year.

Pediatric Safety Pool

The pediatric pooled safety population described in the WARNINGS AND PRECAUTIONS reflects exposure to weight-based TAFINLAR orally, twice daily administered in combination with trametinib in 166 pediatric patients across two trials: a multi-center, open-label, multi-cohort study in pediatric patients with BRAF V600E mutation-positive glioma requiring systemic therapy (Study G2201; n = 123) and a multi-center, open-label, multi-cohort study in pediatric patients with refractory or recurrent solid tumors with MAPK pathway activation (Study X2101; n = 43) [see Clinical Studies (14.6, 14.7)]. Among 166 patients who received TAFINLAR administered with trametinib, 84% were exposed for 6 months or longer and 70% were exposed for greater than one year. The most common (> 20%) adverse reactions were pyrexia (66%), rash (54%), headache (40%), vomiting (38%), musculoskeletal pain (36%), fatigue (31%), dry skin (31%), diarrhea (30%), nausea (26%), epistaxis and other bleeding events (25%), abdominal pain (24%), and dermatitis acneiform (23%). The most common (> 2%) Grade 3 or 4 laboratory abnormalities were decreased neutrophil count (20%), increased alanine aminotransferase (3.1%), and increased aspartate aminotransferase (3.1%).

Unresectable or Metastatic BRAF V600E or V600K Mutation-Positive Melanoma

TAFINLAR as a Single Agent

The safety of TAFINLAR was evaluated in BREAK-3, a multi-center, international, open-label, randomized (3:1), controlled trial that allocated 250 patients with unresectable or metastatic BRAF V600E mutation-positive melanoma to receive TAFINLAR 150 mg orally twice daily (n = 187) or dacarbazine 1000 mg/m^2 intravenously every 3 weeks (n = 63) [see Clinical Studies (14.1)]. The trial excluded patients with abnormal LVEF or cardiac valve morphology (≥ Grade 2), corrected QT interval ≥ 480 milliseconds on electrocardiogram, or a known history of G6PD deficiency. The median duration on treatment was 4.9 months for patients treated with TAFINLAR and 2.8 months for dacarbazine-treated patients. The population exposed to TAFINLAR was 60% male, 99% White, and had a median age of 53 years.

The most common adverse reactions (≥ 20%) in patients treated with TAFINLAR were, in order of decreasing frequency: hyperkeratosis, headache, pyrexia, arthralgia, papilloma, alopecia, and palmar-plantar erythrodysesthesia syndrome (PPES).

The incidence of adverse events resulting in permanent discontinuation of study medication in the BREAK-3 study was 3% for patients treated with TAFINLAR and 3% for patients treated with dacarbazine. The most frequent (≥ 2%) adverse reactions leading to dose reduction of TAFINLAR were pyrexia (9%), PPES (3%), chills (3%), fatigue (2%), and headache (2%). Table 6 and Table 7 present adverse reactions and laboratory abnormalities, respectively, of TAFINLAR as a single agent in the BREAK-3 study.

Table 6. Select Adverse Reactions Occurring in ≥ 10% (All Grades) or ≥ 2% (Grades 3 or 4) of Patients Treated with TAFINLAR in the BREAK-3 Studya
 | TAFINLAR N = 187 |  | Dacarbazine N = 59
Adverse Reactions | All Grades (%) | Grades 3 and 4 b (%) | All Grades (%) | Grades 3 and 4 (%)
Skin and subcutaneous tissue
Hyperkeratosis | 37 | 1 | 0 | 0
Alopecia | 22 | NA | 2 | NA
Palmar-plantar erythrodysesthesia syndrome | 20 | 2 | 2 | 0
Rash | 17 | 0 | 0 | 0
Nervous system
Headache | 32 | 0 | 8 | 0
General
Pyrexia | 28 | 3 | 10 | 0
Musculoskeletal and connective tissue
Arthralgia | 27 | 1 | 2 | 0
Back pain | 12 | 3 | 7 | 0
Myalgia | 11 | 0 | 0 | 0
Neoplasms
Papillomac | 27 | 0 | 2 | 0
cuSCCd | 7 | 4 | 0 | 0
Respiratory system
Cough | 12 | 0 | 5 | 0
Gastrointestinal
Constipation | 11 | 2 | 14 | 0
Infections and infestations
Nasopharyngitis | 10 | 0 | 3 | 0
Abbreviations: cuSCC, cutaneous squamous cell carcinoma, includes squamous cell carcinoma of the skin and keratoacanthoma; NA, not applicable.
a Adverse reactions, reported using MedDRA and graded using NCI CTCAE version 4.0 for assessment of toxicity.
b Grade 4 adverse reactions limited to hyperkeratosis (n = 1) and constipation (n = 1).
c Includes skin papilloma and papilloma.
d Cases of cuSCC were required to be reported as Grade 3 per protocol.

Table 7. Laboratory Abnormalities Worsening from Baseline Occurring at a Higher Incidence in Patients Treated with TAFINLAR in the BREAK-3 Study [Between-Arm Difference of ≥ 5% (All Grades) or ≥ 2% (Grades 3 or 4)]a
 | TAFINLAR N = 187 |  | Dacarbazine N = 59
Laboratory Abnormality | All Grades (%) | Grades 3 and 4 (%) | All Grades (%) | Grades 3 and 4 (%)
Hyperglycemia | 50 | 6 | 43 | 0
Hypophosphatemia | 37 | 6b | 14 | 2
Increased alkaline phosphatase | 19 | 0 | 14 | 2
Hyponatremia | 8 | 2 | 3 | 0
a Adverse reactions, reported using MedDRA and graded using NCI CTCAE version 4.0 for assessment of toxicity.
b Grade 4 laboratory abnormality limited to hypophosphatemia (n = 1).

Other clinically important adverse reactions for TAFINLAR in a pool of TAFINLAR monotherapy clinical studies observed in less than 10% of patients who received TAFINLAR were:

Gastrointestinal: Pancreatitis

Immune System: Hypersensitivity manifesting as bullous rash

Nervous System: Peripheral neuropathy

Renal and Urinary: Interstitial nephritis

Skin and Subcutaneous Tissue: Photosensitivity

TAFINLAR with Trametinib

The safety of TAFINLAR when administered with trametinib was evaluated in 559 patients with previously untreated, unresectable or metastatic, BRAF V600E or V600K mutation-positive melanoma who received TAFINLAR in two trials, the COMBI-d study (n = 209), a multi-center, double-blind, randomized (1:1), active-controlled trial and the COMBI-v study (n = 350), a multi-center, open-label, randomized (1:1), active-controlled trial. In both trials, patients received TAFINLAR 150 mg orally twice daily and trametinib 2 mg orally once daily until disease progression or unacceptable toxicity. Both trials excluded patients with abnormal LVEF, history of acute coronary syndrome within 6 months, history of Class II or greater congestive heart failure (New York Heart Association), history of retinal vein occlusion (RVO) or retinal pigment epithelial detachment (RPED), QTcB interval ≥ 480 msec, treatment refractory hypertension, uncontrolled arrhythmias, active brain metastases, or known history of G6PD deficiency [see Clinical Studies (14.2)].

Among these 559 patients, 199 (36%) were exposed to TAFINLAR for > 6 months to 12 months while 185 (33%) were exposed to TAFINLAR for ≥ 1 year. The median age was 55 years (range: 18 to 91), 57% were male, 98% were White, 72% had baseline ECOG performance status of 0 and 28% had ECOG performance status of 1, 64% had M1c disease, 35% had elevated lactate dehydrogenase (LDH) at baseline, and 0.5% had a history of brain metastases.

The most common adverse reactions (≥ 20%) for TAFINLAR in patients who received TAFINLAR plus trametinib in the COMBI-d and COMBI-v studies were: pyrexia, rash, chills, headache, arthralgia, and cough. The demographics and baseline tumor characteristics of patients enrolled in the COMBI-d study are summarized in Clinical Studies [see Clinical Studies (14.2)]. Patients who received TAFINLAR plus trametinib had a median duration of exposure of 11 months (range: 3 days to 30 months) to TAFINLAR. Among the 209 patients who received TAFINLAR plus trametinib, 26% were exposed to TAFINLAR for > 6 months to 12 months while 46% were exposed to TAFINLAR for > 1 year.

In the COMBI-d study, adverse reactions leading to discontinuation of TAFINLAR occurred in 11% of patients who received TAFINLAR plus trametinib; the most frequent was pyrexia (1.9%). Adverse reactions leading to dose reductions of TAFINLAR occurred in 26% of patients who received TAFINLAR plus trametinib; the most frequent were pyrexia (14%), neutropenia (1.9%), rash (1.9%), and chills (1.9%). Adverse reactions leading to dose interruptions of TAFINLAR occurred in 56% of patients who received TAFINLAR plus trametinib; the most frequent were pyrexia (35%), chills (11%), vomiting (7%), nausea (5%), and decreased ejection fraction (5%).

Table 8 and Table 9 present adverse reactions and laboratory abnormalities, respectively, observed in the COMBI-d study.

Table 8. Select Adverse Reactions Occurring in ≥ 10% (All Grades) of Patients Treated with TAFINLAR Administered with Trametinib in the COMBI-d Studya
 | Pooled TAFINLAR plus Trametinib N = 559 |  | COMBI-d Study
 |  |  | TAFINLAR plus Trametinib N = 209 |  | TAFINLAR N = 211
Adverse Reactions | All Grades (%) | Grades 3 and 4 b (%) | All Grades (%) | Grades 3 and 4 (%) | All Grades (%) | Grades 3 and 4 (%)
General
Pyrexia | 54 | 5 | 57 | 7 | 33 | 1.9
Chills | 31 | 0.5 | 31 | 0 | 17 | 0.5
Skin and subcutaneous tissue
Rashc | 32 | 1.1 | 42 | 0 | 27 | 1.4
Dry skin | 10 | 0 | 12 | 0 | 16 | 0
Nervous system
Headache | 30 | 0.9 | 33 | 0.5 | 30 | 1.4
Dizziness | 11 | 0.2 | 14 | 0 | 7 | 0
Musculoskeletal and connective tissue
Arthralgia | 25 | 0.9 | 26 | 0.9 | 31 | 0
Myalgia | 15 | 0.2 | 13 | 0.5 | 13 | 0
Respiratory system
Cough | 20 | 0 | 21 | 0 | 21 | 0
Gastrointestinal
Constipation | 13 | 0.2 | 13 | 0.5 | 10 | 0
Infections and infestations
Nasopharyngitis | 12 | 0 | 12 | 0 | 10 | 0
a NCI CTCAE version 4.0.
b Grade 4 adverse reactions limited to headache (n = 1).
c Includes rash generalized, rash pruritic, rash erythematous, rash papular, rash vesicular, rash macular, rash maculo-papular, and rash follicular.

Other clinically important adverse reactions for TAFINLAR across the COMBI-d and COMBI-v studies (N = 559) observed in less than 10% of patients who received TAFINLAR administered with trametinib were:

Cardiac: Atrioventricular block, bundle branch block

Gastrointestinal: Colitis, gastrointestinal perforation, pancreatitis

Immune System: Sarcoidosis

Nervous System: Peripheral neuropathy, Guillain-Barré syndrome

Skin and Subcutaneous Tissue: Panniculitis, photosensitivity

Table 9. Select Laboratory Abnormalities Worsening from Baseline Occurring at ≥ 10% (All Grades) of Patients Who Received TAFINLAR with Trametinib in the COMBI-d Study
Laboratory Abnormalities | Pooled TAFINLAR plus Trametinib N = 559 a |  | COMBI-d Study
 |  |  | TAFINLAR plus Trametinib N = 209 b |  | TAFINLAR N = 211 b
 | All Grades (%) | Grades 3 and 4 c (%) | All Grades (%) | Grades 3 and 4 c (%) | All Grades (%) | Grades 3 and 4 c (%)
Chemistry
Hyperglycemia | 60 | 4.7 | 65 | 6 | 57 | 4.3
Hypophosphatemia | 38 | 6 | 38 | 3.8 | 35 | 7
Hyponatremia | 25 | 8 | 24 | 6 | 14 | 2.9
Hepatic
Increased blood alkaline phosphatase | 49 | 2.7 | 50 | 1.0 | 25 | 0.5
a For these laboratory tests, the denominator is 556.
b For these laboratory tests, the denominator is 208 for the combination arm, 208-209 for the TAFINLAR arm.
c Grade 4 adverse reactions limited to hyperglycemia (n = 4), hyponatremia and hypophosphatemia (each n = 1) in the pooled combination arm; hyperglycemia (n = 1) in the COMBI-d study combination arm; hypophosphatemia (n = 1) in the TAFINLAR arm.

Adjuvant Treatment of BRAF V600E or V600K Mutation-Positive Melanoma

The safety of TAFINLAR when administered with trametinib was evaluated in 435 patients with Stage III melanoma with BRAF V600E or V600K mutations following complete resection who received at least one dose of study therapy in the COMBI-AD study [see Clinical Studies (14.3)]. Patients received TAFINLAR 150 mg orally twice daily and trametinib 2 mg orally once daily for 12 months. The trial excluded patients with abnormal LVEF; history of acute coronary syndromes, coronary angioplasty, or stenting within 6 months; Class II or greater congestive heart failure (New York Heart Association); QTc interval ≥ 480 msec; treatment refractory hypertension; uncontrolled arrhythmias; or history of RVO.

Patients who received TAFINLAR in combination with trametinib had a median duration of exposure of 11 months (range: 0 to 12) to TAFINLAR. Among the 435 patients receiving TAFINLAR in combination with trametinib, 71% were exposed to TAFINLAR for > 6 months. The median age of patients who received TAFINLAR administered with trametinib was 50 years (range: 18 to 89), 56% were male, 99% were White, 92% had baseline ECOG performance status of 0, and 8% had baseline ECOG performance status of 1.

The most common adverse reactions (≥ 20%) in patients who received TAFINLAR administered with trametinib were: pyrexia, fatigue, nausea, headache, rash, chills, diarrhea, vomiting, arthralgia, and myalgia.

Adverse reactions resulting in discontinuation, dose reduction, or dose interruption of TAFINLAR occurred in 25%, 35%, and 66% of patients, respectively; the most frequent for each were pyrexia and chills.

Table 10 summarizes the adverse reactions that occurred in at least 20% of patients who received TAFINLAR administered with trametinib.

Table 10. Adverse Reactions Occurring in ≥ 20% of Patients in the COMBI-AD Studya
Adverse Reactions | TAFINLAR plus Trametinib N = 435 |  | Placebo N = 432
 | All Grades (%) | Grades 3 and 4 (%) | All Grades (%) | Grades 3 and 4 (%)
General
Pyrexiab | 63 | 5 | 11 | < 1
Fatiguec | 59 | 5 | 37 | < 1
Chills | 37 | 1 | 4 | 0
Gastrointestinal
Nausea | 40 | < 1 | 20 | 0
Diarrhea | 33 | < 1 | 15 | < 1
Vomiting | 28 | < 1 | 10 | 0
Nervous system
Headached | 39 | 1 | 24 | 0
Skin and subcutaneous tissue
Rashe | 37 | < 1 | 16 | < 1
Musculoskeletal and connective tissue
Arthralgia | 28 | < 1 | 14 | 0
Myalgiaf | 20 | < 1 | 14 | 0
a NCI CTCAE version 4.0.
b Includes pyrexia and hyperpyrexia.
c Includes fatigue, asthenia, and malaise.
d Includes headache and tension headache.
e Includes rash, rash maculo-papular, rash macular, rash generalized, rash erythematous, rash papular, rash pruritic, nodular rash, rash vesicular, and rash pustular.
f Includes myalgia, musculoskeletal pain, and musculoskeletal chest pain.

Other clinically important adverse reactions for TAFINLAR in the COMBI-AD study observed in less than 20% of patients who received TAFINLAR administered with trametinib were: blurred vision (6%), decreased ejection fraction (5%), peripheral neuropathy (2.5%), rhabdomyolysis (< 1%), atrioventricular block (< 1%), Guillain-Barré syndrome (< 1%), and sarcoidosis (< 1%).

The laboratory abnormalities are summarized in Table 11.

Table 11. Laboratory Abnormalities Worsening from Baseline Occurring in ≥ 20% of Patients in the COMBI-AD Study
Laboratory Abnormality | TAFINLAR plus Trametiniba N = 435 |  | Placeboa N = 432
 | All Grades (%) | Grades 3 and 4 (%) | All Grades (%) | Grades 3 and 4 (%)
Chemistry
Hyperglycemia | 63 | 3 | 47 | 2
Hypophosphatemia | 42 | 7 | 10 | < 1
Hypoalbuminemia | 25 | < 1 | < 1 | 0
Hepatic
Increased AST | 57 | 6 | 11 | < 1
Increased ALT | 48 | 5 | 18 | < 1
Increased blood alkaline phosphatase | 38 | 1 | 6 | < 1
Hematology
Neutropenia | 47 | 6 | 12 | < 1
Lymphopenia | 26 | 5 | 6 | < 1
Anemia | 25 | < 1 | 6 | < 1
Abbreviations: ALT, alanine aminotransferase; AST, aspartate aminotransferase.
a The incidence is based on the number of patients who had both a baseline and at least one on-study laboratory measurement:
TAFINLAR plus Trametinib (range: 429 to 431) and Placebo arm (range: 426 to 428).

Trial COMBI-aPlus (Pyrexia Management Study)

COMBI-aPlus evaluated the impact of pyrexia-related outcomes of a revised pyrexia management algorithm in patients who received dabrafenib administered with trametinib in the adjuvant treatment of BRAF V600 mutation-positive melanoma after complete resection. The pyrexia management algorithm interrupted both dabrafenib and trametinib when patient’s temperature is ≥ 100.4°F.

Grade 3-4 pyrexia occurred in 4.3% of patients, hospitalizations due to pyrexia occurred in 5.1% of patients, pyrexia with complications (dehydration, hypotension, renal dysfunction, syncope, severe chills) occurred in 2.2% of patients, and treatment discontinuation due to pyrexia occurred in 2.5% of patients.

Metastatic, BRAF V600E Mutation-Positive Non-Small Cell Lung Cancer

The safety of TAFINLAR when administered with trametinib was evaluated in 93 patients with previously untreated (n = 36) and previously treated (n = 57) metastatic BRAF V600E mutation-positive NSCLC in a multi-center, multi-cohort, non-randomized, open-label trial (Study BRF113928). Patients received TAFINLAR 150 mg orally twice daily and trametinib 2 mg orally once daily until disease progression or unacceptable toxicity. The trial excluded patients with abnormal LVEF, history of acute coronary syndrome within 6 months, history of Class II or greater congestive heart failure (New York Heart Association), QTc interval ≥ 480 msec, treatment refractory hypertension, uncontrolled arrhythmias, active brain metastases, history of interstitial lung disease or pneumonitis, or history or current RVO [see Clinical Studies (14.4)].

Among these 93 patients, 53 (57%) were exposed to TAFINLAR and trametinib for > 6 months and 27 (29%) were exposed to TAFINLAR and trametinib for ≥ 1 year. The median age was 65 years (range: 41 to 91); 46% were male; 85% were White; 32% had baseline ECOG performance status of 0 and 61% had ECOG performance status of 1; 98% had non-squamous histology; and 12% were current smokers, 60% were former smokers, and 28% had never smoked.

The most common adverse reactions (≥ 20%) in these 93 patients were: pyrexia, fatigue, nausea, vomiting, diarrhea, dry skin, decreased appetite, edema, rash, chills, hemorrhage, cough, and dyspnea.

Adverse reactions leading to discontinuation of TAFINLAR occurred in 18% of patients; the most frequent were pyrexia (2.2%), decreased ejection fraction (2.2%), and respiratory distress (2.2%). Adverse reactions leading to dose reductions of TAFINLAR occurred in 35% of patients; the most frequent were pyrexia (10%), diarrhea (4.3%), nausea (4.3%), vomiting (4.3%), and neutropenia (3.2%). Adverse reactions leading to dose interruptions of TAFINLAR occurred in 62% of patients; the most frequent were pyrexia (27%), vomiting (11%), neutropenia (8%), and chills (6%).

Table 12 and Table 13 present adverse reactions and laboratory abnormalities, respectively, of TAFINLAR administered with trametinib in Study BRF113928.

Table 12. Adverse Reactions Occurring in ≥ 20% (All Grades) of Patients Treated with TAFINLAR Administered with Trametinib in Study BRF113928a
Adverse Reactions | TAFINLAR plus Trametinib N = 93
 | All Grades (%) | Grades 3 and 4 (%)
General
Pyrexia | 55 | 5
Fatigueb | 51 | 5
Edemac | 28 | 0
Chills | 23 | 1.1
Gastrointestinal
Nausea | 45 | 0
Vomiting | 33 | 3.2
Diarrhea | 32 | 2.2
Decreased appetite | 29 | 0
Skin and subcutaneous tissue
Dry skin | 31 | 1.1
Rashd | 28 | 3.2
Vascular
Hemorrhagee | 23 | 3.2
Respiratory system
Cough | 22 | 0
Dyspnea | 20 | 5
a NCI CTCAE version 4.0.
b Includes fatigue, malaise, and asthenia.
c Includes peripheral edema, edema, and generalized edema.
d Includes rash, rash generalized, rash papular, rash macular, rash maculo-papular, and rash pustular.
e Includes hemoptysis, hematoma, epistaxis, purpura, hematuria, subarachnoid hemorrhage, gastric hemorrhage, urinary bladder hemorrhage, contusion, hematochezia, injection site hemorrhage, pulmonary hemorrhage, and retroperitoneal hemorrhage.

Other clinically important adverse reactions for TAFINLAR in Study BRF113928 observed in less than 20% of patients who received TAFINLAR administered with trametinib were:

Cardiac: Atrioventricular block

Gastrointestinal: Pancreatitis

Nervous System: Peripheral neuropathy

Renal and Urinary: Tubulointerstitial nephritis

Table 13. Treatment-Emergent Laboratory Abnormalities Occurring in ≥ 20% (All Grades) of Patients Who Received TAFINLAR with Trametinib in Study BRF113928
Laboratory Abnormality | TAFINLAR plus Trametinib N = 93
 | All Grades (%) | Grades 3 and 4 (%)
Chemistrya
Hyperglycemia | 71 | 9
Hyponatremia | 57 | 17
Hypophosphatemia | 36 | 7
Increased creatinine | 21 | 1.1
Hepatica
Increased blood alkaline phosphatase | 64 | 0
Increased AST | 61 | 4.4
Increased ALT | 32 | 6
Hematologyb
Leukopenia | 48 | 8
Anemia | 46 | 10
Neutropenia | 44 | 8
Lymphopenia | 42 | 14
Abbreviations: ALT, alanine aminotransferase; AST, aspartate aminotransferase.
a For these laboratory tests, the denominator is 90.
b For these laboratory tests, the denominator is 91.

Advanced BRAF V600E Mutation-Positive Tumors

Study BRF117019

The safety of TAFINLAR when administered with trametinib was evaluated in a multi-cohort, multi-center, non-randomized, open-label study in adult patients with cancers with the BRAF V600E mutation (Study BRF117019). A total of 206 patients were enrolled in the trial, 36 of whom were enrolled in the ATC cohort, 105 were enrolled in specific solid tumor cohorts, and 65 in other malignancies [see Clinical Studies (14.5, 14.6)]. Patients received TAFINLAR 150 mg orally twice daily and trametinib 2 mg orally once daily until disease progression or unacceptable toxicity.

Among these 206 patients, 103 (50%) were exposed to TAFINLAR for ≥ 1 year and 101 (49%) were exposed to trametinib for ≥ 1 year. The median age was 60 years (range: 18 to 89); 56% were male; 79% were White; and 34% had baseline ECOG performance status of 0 and 60% had ECOG performance status of 1.

Serious adverse reactions occurred in 45% of patients who received TAFINLAR in combination with trametinib. Serious adverse reactions in > 5% of patients included pyrexia (11%) and pneumonia (6%). Fatal adverse reactions occurred in 3.9% of patients who received TAFINLAR in combination with trametinib. Fatal adverse reactions that occurred in > 1% of patients included sepsis (1.9%).

Permanent treatment discontinuation due to an adverse reaction occurred in 13% of patients. Adverse reactions which resulted in permanent treatment discontinuation in > 1% of patients included nausea (1.5%).

Dosage interruptions due to an adverse reaction occurred in 55% of patients. Adverse reactions which required dosage interruption in > 5% of patients included pyrexia (22%), chills (9%), fatigue (6%), neutropenia (6%), and nausea (5%).

Dose reductions due to an adverse reaction occurred in 44% of patients. Adverse reactions which required dose reductions in > 5% of patients included pyrexia (18%), chills (8%), and fatigue (6%).

The most common (≥ 20%) adverse reactions, including laboratory abnormalities, are listed in Table 14 and Table 15.

Table 14 summarizes the adverse reactions in Study BRF117019.

Table 14. Adverse Reactions (≥ 20%) in Adult Patients Treated with TAFINLAR Plus Trametinib in Study BRF117019
Adverse Reactions | TAFINLAR plus Trametiniba (N = 206)
 | All Grades (%) | Grade 3 or 4 (%)
General
Pyrexia | 55 | 4.9
Fatigueb | 50 | 5
Chills | 30 | 0.5
Peripheral edemac | 22 | 0
Gastrointestinal
Nausea | 40 | 1.5
Constipation | 27 | 0
Vomiting | 27 | 1.5
Diarrhea | 26 | 2.9
Skin and subcutaneous tissue
Rashd | 40 | 2.4
Nervous system
Headache | 30 | 1.5
Vascular
Hemorrhagee | 29 | 4.4
Respiratory system
Coughf | 29 | 0
Musculoskeletal and connective tissue
Myalgiag | 24 | 0.5
Arthralgia | 23 | 0.5
aNCI CTCAE version 4.0.
bIncludes fatigue, asthenia, and malaise.
cIncludes peripheral edema and peripheral swelling.
dIncludes rash, rash maculo-papular, rash erythematous, rash pustular, and rash papular.
eIncludes epistaxis, hematuria, contusion, hematoma, hemoptysis, conjunctival hemorrhage, hematochezia, rectal hemorrhage, hemorrhoidal hemorrhage, melena, purpura, eye contusion, eye hemorrhage, gastric hemorrhage, gingival bleeding, hematemesis, hemorrhage intracranial, hemorrhagic stroke, hemothorax, increased tendency to bruise, large intestinal hemorrhage, mouth hemorrhage, petechiae, pharyngeal hemorrhage, prothrombin time prolonged, pulmonary hematoma, retinal hemorrhage, vaginal hemorrhage, and vitreous hemorrhage.
fIncludes cough and productive cough.
gIncludes myalgia, musculoskeletal chest pain, and musculoskeletal pain.

Clinically relevant adverse reactions for TAFINLAR in Study BRF117019 observed in less than 20% of patients who received TAFINLAR in combination with trametinib were: peripheral neuropathy (9%), decreased ejection fraction (8%), atrioventricular block (2.9%), uveitis (1.9%), hypersensitivity (1.9%), and Guillain-Barré syndrome (< 1%).

Table 15 summarizes the laboratory abnormalities in Study BRF117019.

Table 15. Select Laboratory Abnormalities (≥ 20%) That Worsened from Baseline in Adult Patients Treated with TAFINLAR Plus Trametinib in Study BRF117019
Laboratory Abnormality | TAFINLAR plus Trametiniba
 | All Grades (%) | Grade 3 or 4 (%)
Chemistry
Hyperglycemia | 61 | 8
Decreased sodium | 35 | 10
Decreased magnesium | 24 | 0
Increased creatinine | 21 | 1.5
Hepatic
Increased alkaline phosphatase | 51 | 5
Increased AST | 51 | 4.6
Increased ALT | 39 | 3
Hematology
Decreased hemoglobin | 44 | 9
Abbreviations: ALT, alanine aminotransferase; AST, aspartate aminotransferase.
a The denominator used to calculate the rate varied from 199 to 202 based on the number of patients with a baseline value and at least one post-treatment value.

BRAF V600E Mutation-Positive Solid Tumors in Pediatric Patients
Study CTMT212X2101 (X2101)

The safety of TAFINLAR when administered with trametinib was evaluated in Study X2101, a multi-center, open-label, multi-cohort study in pediatric patients (n = 48) with refractory or recurrent solid tumors [see Clinical Studies (14.6)]. The median duration of exposure to TAFINLAR in Parts C (dose escalation) and D (cohort expansion) was 20.8 and 24.9 months, respectively. The median duration of exposure to trametinib in Parts C and D was 20.8 and 24.4 months, respectively. The median age of pediatric patients who received TAFINLAR with trametinib was 9 years (range: 1 to 17).

Serious adverse reactions occurred in 46% of patients who received TAFINLAR in combination with trametinib. Serious adverse reactions in > 5% of patients included pyrexia (25%) and decreased ejection fraction (6%). Permanent treatment discontinuation due to an adverse reaction occurred in 21% of patients. Adverse reactions which resulted in permanent treatment discontinuation in > 3% of patients included increased ALT (6%), increased AST (4.2%) and decreased ejection fraction (4.2%). Dosage interruptions due to an adverse reaction occurred in 73% of patients. Adverse reactions which required dosage interruption in > 5% of patients included pyrexia (56%), vomiting (19%), neutropenia (13%), rash (13%), decreased ejection fraction (6%), and uveitis (6%). Dose reductions due to an adverse reaction occurred in 25% of patients. Adverse reactions which required dose reductions in > 5% of patients included pyrexia (13%).

The most common (≥ 20%) adverse reactions, including laboratory abnormalities, are listed in Table 16 and Table 17.

Table 16 summarizes the adverse reactions in Study X2101.

Table 16. Adverse Reactions (≥ 20%) in Pediatric Patients Treated with TAFINLAR Plus Trametinib in Study X2101a
Adverse Reactions | TAFINLAR plus Trametiniba (N = 48)
 | All Grades (%) | Grade 3 or 4 (%)
General
Pyrexia | 75 | 17
Fatigueb | 48 | 0
Skin and subcutaneous tissue
Rashc | 73 | 2.1
Dry skin | 48 | 0
Dermatitis acneiformd | 40 | 0
Gastrointestinal
Vomiting | 52 | 4.2
Diarrhea | 42 | 2.1
Abdominal paine | 33 | 4.2
Nausea | 33 | 2.1
Constipation | 23 | 0
Respiratory system
Cough | 44 | 0
Nervous system
Headache | 35 | 0
Vascular
Hemorrhagef | 33 | 0
Infections and infestations
Paronychia | 23 | 0
a NCI CTCAE version 4.0.
b Includes fatigue, asthenia, and malaise.
c Includes rash, rash maculo-papular, rash erythematous, rash papular, rash pustular, and rash macular.
d Includes dermatitis acneiform and acne.
e Includes abdominal pain and abdominal pain upper.
f Includes epistaxis, hematuria, contusion, hematoma, petechiae, rectal hemorrhage, and red blood cell count decreased.

Clinically relevant adverse reactions for TAFINLAR in Study X2101 observed in less than 20% of patients (N=48) who received TAFINLAR in combination with trametinib were: atrioventricular block (2.1%).

Table 17 summarizes the laboratory abnormalities in Study X2101.

Table 17. Select Laboratory Abnormalities (≥ 20%) That Worsened from Baseline in Pediatric Patients Treated with TAFINLAR Plus Trametinib in Study X2101
Laboratory Abnormality | TAFINLAR plus Trametiniba
 | All Grades (%) | Grade 3 or 4 (%)
Chemistry
Hyperglycemia | 65 | 2.2
Hypoalbuminemia | 48 | 2.1
Hypocalcemia | 40 | 2.1
Decreased phosphate | 38 | 0
Decreased magnesium | 33 | 2.1
Hypernatremia | 27 | 0
Hypokalemia | 21 | 2.1
Hepatic
Increased AST | 55 | 4.2
Increased ALT | 40 | 6
Increased alkaline phosphatase | 28 | 6
Increased total bilirubin | 21 | 2.1
Hematology
Decreased hemoglobin | 60 | 6
Decreased neutrophils | 49 | 28
Abbreviations: ALT, alanine aminotransferase; AST, aspartate aminotransferase.
aThe denominator used to calculate the rate varied from 39 to 48 based on the number of patients with a baseline value and at least one post-treatment value.

BRAF V600E Mutation-Positive Low-Grade Glioma in Pediatric Patients

Study CDRB436G2201 (G2201)

The safety of TAFINLAR in combination with trametinib was evaluated in pediatric patients 1 to < 18 years of age in Study G2201. Patients with low-grade glioma (LGG) who required first systemic therapy were randomized (2:1) to TAFINLAR plus trametinib (n = 73) or carboplatin plus vincristine (n = 33). Nine patients crossed over from the carboplatin plus vincristine arm to the TAFINLAR and trametinib arm. Pediatric patients received weight-based TAFINLAR orally twice daily administered in combination with trametinib until disease progression or intolerable toxicity. Patients in the control arm received carboplatin and vincristine at doses of 175 mg/m^2 and 1.5 mg/m^2, respectively in 10-week induction course followed by eight 6-week cycles of maintenance therapy or until disease progression or intolerable toxicity. Among patients with low-grade glioma who were randomized to TAFINLAR plus trametinib (n = 73), 95% were exposed for 6 months or longer and 71% were exposed for greater than one year.

The median age of these patients was 10 years (range: 1 to 17); 60% female; 75% White, 7% Asian, 2.7% Black or African American, 4% other race, and 11% where race was unknown or not reported.

Serious adverse reactions occurred in 40% of these patients. Serious adverse reactions in > 3% of patients included pyrexia (14%) and vomiting (4%).

Permanent discontinuation of TAFINLAR due to an adverse reaction occurred in 4% of patients. Adverse reactions which resulted in permanent discontinuation of TAFINLAR included chills, fatigue, pyrexia, weight increased, and headache.

Dosage interruptions of TAFINLAR due to an adverse reaction occurred in 73% of patients. Adverse reactions which required dosage interruption in > 5% of patients included pyrexia (53%).

Dose reductions of TAFINLAR due to an adverse reaction occurred in 48% of patients. Adverse reactions which required dose reductions in > 2% of patients included rash (2.7%). The most common (≥ 15%) adverse reactions were pyrexia (68%), rash (51%), headache (47%), vomiting (34%), musculoskeletal pain (34%), fatigue (33%), diarrhea (29%), dry skin (26%), nausea (25%), hemorrhage (25%), abdominal pain (25%), dermatitis acneiform (22%), dizziness (15%), upper respiratory tract infection (15%), and weight increased (15%).

The most common (≥ 20%) laboratory abnormalities that worsened from baseline were leukopenia (59%), increased alkaline phosphatase (55%), anemia (46%), decreased neutrophils (44%), increased AST (37%), decreased magnesium (34%), increased magnesium (32%), decreased platelets (30%), increased ALT (29%), and increased lymphocytes (24%).

Table 18 summarizes the adverse reactions in Study G2201.

Table 18. Adverse Reactions (≥ 15%) in Pediatric LGG Patients Who Received TAFINLAR in Combination with Trametinib in Study G2201a
Adverse Reactions | TAFINLAR plus Trametinib N = 73 |  | Carboplatin plus Vincristine N = 33
 | All Grades (%) | Grade ≥ 3 (%) | All Grades (%) | Grade ≥ 3 (%)
Gastrointestinal
Vomiting | 34 | 1 | 48 | 3
Diarrheab | 29 | 0 | 18 | 6
Nausea | 25 | 0 | 45 | 0
Abdominal painc | 25 | 0 | 24 | 0
Constipation | 12 | 0 | 36 | 0
Stomatitisd | 10 | 0 | 18 | 0
General
Pyrexiae | 68 | 8 | 18 | 3
Fatiguef | 33 | 0 | 39 | 0
Nervous system
Headacheg | 47 | 1 | 33 | 3
Dizzinessh | 15 | 0 | 9 | 3
Peripheral neuropathyi | 7 | 0 | 45 | 6
Vascular
Hemorrhagej | 25 | 0 | 12 | 0
Skin and subcutaneous tissue
Rashk | 51 | 2.7 | 18 | 3
Dry skin | 26 | 0 | 3 | 0
Dermatitis acneiforml | 22 | 0 | 0 | 0
Alopecia | 3 | 0 | 24 | 0
Musculoskeletal and connective tissue
Musculoskeletal painm | 34 | 0 | 30 | 0
Pain in jaw | 1.4 | 0 | 18 | 0
Metabolism and nutrition
Decreased appetite | 5 | 0 | 24 | 0
Respiratory, thoracic and mediastinal
Oropharyngeal pain | 11 | 0 | 18 | 0
Psychiatric
Anxiety | 1.4 | 0 | 15 | 3
Immune system
Hypersensitivity | 0 | 0 | 15 | 3
Infections and infestations
Upper respiratory tract infection | 15 | 0 | 6 | 0
Injury, poisoning and procedural complications
Infusion-related reaction | 0 | 0 | 15 | 3
Investigations
Weight increased | 15 | 7 | 0 | 0
a NCI CTCAE version 4.03.
b Includes diarrhea, colitis, enterocolitis, and enteritis.
c Includes abdominal pain and upper abdominal pain.
d Includes stomatitis, cheilitis, mouth ulceration, aphthous ulcer, and glossitis.
e Includes pyrexia and body temperature increased.
f Includes fatigue and asthenia.
g Includes headache and migraine with aura.
h Includes dizziness and vertigo.
i Includes peripheral neuropathy, peripheral motor neuropathy, peripheral sensorimotor neuropathy, paresthesia, neuralgia, hypoaesthesia, and peripheral sensory neuropathy.
j Includes epistaxis, post-procedural hemorrhage, hematuria, upper gastrointestinal hemorrhage, and hemorrhage intracranial.
k Includes rash, rash macular, rash maculo-papular, rash pustular, rash papular, rash erythematous, eczema, erythema multiforme, dermatitis, dermatitis exfoliative, skin exfoliation, palmar-plantar erythrodysaesthesia syndrome, and dermatitis bullous.
l Includes dermatitis acneiform, acne, and acne pustular.
m Includes back pain, myalgia, pain in extremity, arthralgia, bone pain, non-cardiac chest pain, neck pain, and musculoskeletal stiffness.

Table 19 summarizes the laboratory abnormalities in Study G2201.

Table 19. Select Laboratory Abnormalities (≥ 20%) That Worsened from Baseline in Pediatric LGG Patients Who Received TAFINLAR in Combination with Trametinib in Study G2201a
Laboratory Abnormality | TAFINLAR plus Trametinib N = 73 |  | Carboplatin plus Vincristine N = 33
 | All Grades (%) | Grade 3 or 4 (%) | All Grades (%) | Grade 3 or 4 (%)
Hepatic
Increased alkaline phosphatase | 55 | 0 | 13 | 0
Increased AST | 37 | 1.4 | 55 | 0
Increased ALT | 29 | 3 | 61 | 9
Chemistry
Decreased magnesium | 34 | 4.1 | 76 | 6
Increased magnesium | 32 | 0 | 24 | 3
Increased potassium | 15 | 4.2 | 21 | 6
Decreased calcium | 14 | 4.1 | 22 | 9
Decreased potassium | 8 | 1.4 | 70 | 0
Decreased phosphate | 7 | 2.7 | 33 | 3
Decreased sodium | 5 | 1.4 | 27 | 6
Increased serum fasting glucose | 0 | 0 | 44 | 0
Hematology
Decreased leukocytes | 59 | 0 | 91 | 18
Decreased hemoglobin | 46 | 0 | 94 | 36
Decreased neutrophils | 44 | 17 | 84 | 75
Decreased platelets | 30 | 0 | 73 | 18
Increased lymphocytes | 24 | 0 | 13 | 3.1
Decreased lymphocytes | 16 | 1.4 | 56 | 6
Abbreviations: ALT, alanine aminotransferase; AST, aspartate aminotransferase.
a The denominator used to calculate the rate varied from 70 to 73 in D + T arm and 9 to 33 in C + V arm based on the number of patients with a baseline value and at least one post-treatment value.

6.2 Postmarketing Experience

The following adverse reactions have been identified during post approval use of TAFINLAR in combination with trametinib. Because these reactions are reported voluntarily from a population of uncertain size, it is not always possible to reliably estimate their frequency or establish a causal relationship to drug exposure.

Cardiac: Atrioventricular block complete

Immune System: Hemophagocytic lymphohistiocytosis (HLH) [see Warnings and Precautions (5.11)]

Skin and Subcutaneous Tissue: SCAR (including DRESS and SJS) [see Warnings and Precautions (5.7)]

7 DRUG INTERACTIONS

7.1 Effects of Other Drugs on TAFINLAR

Strong inhibitors of CYP3A4 or CYP2C8 may increase the concentration of dabrafenib [see Clinical Pharmacology (12.3)]. Substitution of strong inhibitors of CYP3A4 or CYP2C8 is recommended during treatment with TAFINLAR. If concomitant use of strong inhibitors of CYP3A4 or CYP2C8 is unavoidable, monitor patients closely for adverse reactions when taking strong inhibitors.

7.2 Effects of TAFINLAR on Other Drugs

Dabrafenib decreased the systemic exposures of midazolam (a CYP3A4 substrate), S-warfarin (a CYP2C9 substrate), and R-warfarin (a CYP3A4/CYP1A2 substrate) [see Clinical Pharmacology (12.3)]. Monitor international normalized ratio (INR) levels more frequently in patients receiving warfarin during initiation or discontinuation of dabrafenib. Coadministration of TAFINLAR with other substrates of these enzymes, including dexamethasone or hormonal contraceptives, can result in decreased concentrations and loss of efficacy [see Use in Specific Populations (8.1, 8.3)]. Substitute for these medications or monitor patients for loss of efficacy if use of these medications is unavoidable.

8 USE IN SPECIFIC POPULATIONS

8.1 Pregnancy

Risk Summary

Based on findings from animal reproduction studies and its mechanism of action [see Clinical Pharmacology (12.1)], TAFINLAR can cause fetal harm when administered to a pregnant woman. There is insufficient data in pregnant women exposed to TAFINLAR to assess the risks. Dabrafenib was teratogenic and embryotoxic in rats at doses three times greater than the human exposure at the recommended adult clinical dose of 150 mg twice daily (see Data). Advise pregnant women of the potential risk to a fetus.

In the U.S. general population, the estimated background risk of major birth defects and miscarriage in clinically recognized pregnancies is 2% to 4% and 15% to 20%, respectively.

Data

Animal Data

In a combined female fertility and embryo-fetal development study in rats conducted during the period of organogenesis, developmental toxicity consisted of embryo-lethality, ventricular septal defects, and variation in thymic shape at a dabrafenib dose of 300 mg/kg/day [approximately three times the human exposure at the recommended adult dose based on area under the curve (AUC)]. At doses of 20 mg/kg/day or greater (equivalent to the human exposure at the recommended adult dose based on AUC), rats demonstrated delays in skeletal development and reduced fetal body weight.

8.2 Lactation

Risk Summary

There are no data on the presence of dabrafenib in human milk, or the effects of dabrafenib on the breastfed child or on milk production. Because of the potential for serious adverse reactions in breastfed children, advise women not to breastfeed during treatment with TAFINLAR and for 2 weeks following the last dose.

8.3 Females and Males of Reproductive Potential

Pregnancy Testing

Verify pregnancy status in females of reproductive potential prior to initiating TAFINLAR.

Contraception

Based on data from animal studies and its mechanism of action, TAFINLAR can cause fetal harm when administered to pregnant women [see Use in Specific Populations (8.1)].

Females

Advise female patients of reproductive potential to use effective contraception during treatment with TAFINLAR and for 2 weeks after the last dose. Counsel patients to use a non-hormonal method of contraception since TAFINLAR can render hormonal contraceptives ineffective [see Drug Interactions (7.2)].

Males

To avoid potential drug exposure to pregnant partners and female partners of reproductive potential, advise male patients (including those who have had vasectomies) with female partners of reproductive potential to use condoms during treatment with TAFINLAR and for 2 weeks after the last dose.

Infertility

Females

Advise female patients of reproductive potential that TAFINLAR may impair fertility. A reduction in fertility was observed in female rats at dose exposures equivalent to the human exposure at the recommended adult dose. A reduction in the number of corpora lutea was noted in pregnant rats at dose exposures approximately three times the human exposure at the recommended adult dose [see Nonclinical Toxicology (13.1)].

Males

Advise male patients of the potential risk for impaired spermatogenesis which may be irreversible. Effects on spermatogenesis have been observed in animals treated with dabrafenib at dose exposures up to three times the human exposure at the recommended adult dose [see Nonclinical Toxicology (13.1)].

8.4 Pediatric Use

BRAF V600E Mutation-Positive Unresectable or Metastatic Solid Tumors and LGG

The safety and effectiveness of TAFINLAR in combination with trametinib have been established in pediatric patients 1 year of age and older with unresectable or metastatic solid tumors with BRAF V600E mutation who have progressed following prior treatment and have no satisfactory alternative treatment options; or with LGG with BRAF V600E mutation who require systemic therapy. Use of TAFINLAR in combination with trametinib for these indications is supported by evidence from studies X2101 and G2201 that enrolled 171 patients (1 to < 18 years of age) with BRAF V600 mutation-positive advanced solid tumors, of which 4 (2.3%) patients were 1 to < 2 years of age, 39 (23%) patients were 2 to < 6 years of age, 54 (32%) patients were 6 to < 12 years of age, and 74 (43%) patients were 12 to < 18 years of age [see Adverse Reactions (6.1), Clinical Pharmacology (12.3), Clinical Studies (14.6, 14.7)].

The safety and effectiveness of TAFINLAR in combination with trametinib have not been established for these indications in pediatric patients less than 1 year old.

The safety and effectiveness of TAFINLAR as a single agent in pediatric patients have not been established.

Juvenile Animal Toxicity Data

In a repeat-dose toxicity study in juvenile rats, an increased incidence of kidney cysts and tubular deposits were noted at doses as low as 0.2 times the human exposure at the recommended adult dose based on AUC. Additionally, forestomach hyperplasia, decreased bone length, and early vaginal opening were noted at doses as low as 0.8 times the human exposure at the recommended adult dose based on AUC.

8.5 Geriatric Use

Of the 586 patients with various solid tumors who received single agent TAFINLAR, 22% were aged 65 years and older. Of the 187 patients with melanoma who received single-agent TAFINLAR in the BREAK-3 study, 21% were aged 65 years and older [see Clinical Studies (14.1)]. No overall differences in the effectiveness or safety of TAFINLAR were observed between geriatric patients as compared to younger adults in the BREAK-3 study.

Of the 994 patients with melanoma who received TAFINLAR plus trametinib in the COMBI-d, COMBI-v, and COMBI-AD studies [see Clinical Studies (14.2, 14.3)], 21% were aged 65 years and older and 5% were aged 75 years and older. No overall differences in the effectiveness of TAFINLAR plus trametinib were observed in geriatric patients as compared to younger adults across these melanoma studies. The incidences of peripheral edema (26% vs. 12%) and anorexia (21% vs. 9%) were increased in geriatric patients as compared to younger adults in these studies.

Of the 171 patients with NSCLC who received TAFINLAR in Study BRF113928, there were insufficient numbers of geriatric patients to determine whether they respond differently from younger adults [see Clinical Studies (14.4)].

Of the 26 patients with ATC who received TAFINLAR in Study BRF117019, 77% were aged 65 years and older, and 31% were aged 75 years and older [see Clinical Studies (14.5)]. This study in ATC did not include sufficient numbers of younger adults to determine whether they respond differently compared to geriatric patients.

8.6 Hepatic Impairment

Dose adjustment is not recommended for patients with mild (bilirubin ≤ upper limit of normal (ULN) and aspartate aminotransferase (AST) > ULN or bilirubin > 1x to 1.5x ULN and any AST) hepatic impairment. As hepatic metabolism and biliary secretion are the primary routes of elimination of dabrafenib and its metabolites, patients with moderate (bilirubin > 1.5x to 3x ULN and any AST) to severe (bilirubin > 3x to 10x ULN and any AST) hepatic impairment may have increased exposure. An appropriate dosage has not been established for patients with moderate to severe hepatic impairment [see Clinical Pharmacology (12.3)].

10 OVERDOSAGE

There is no information on overdosage of TAFINLAR. Since dabrafenib is highly bound to plasma proteins, hemodialysis is likely to be ineffective in the treatment of overdose with TAFINLAR.

11 DESCRIPTION

Dabrafenib mesylate is a kinase inhibitor. The chemical name for dabrafenib mesylate is N-{3-[5-(2-amino-4-pyrimidinyl)-2-(1,1-dimethylethyl)-1,3-thiazol-4-yl]-2-fluorophenyl}-2,6-difluorobenzene sulfonamide, methanesulfonate salt. It has the molecular formula C23H20F3N5O2S2•CH4O3S and a molecular weight of 615.68 g/mol. Dabrafenib mesylate has the following chemical structure:

Dabrafenib mesylate is a white to slightly colored solid with three pKas: 6.6, 2.2, and -1.5. It is very slightly soluble at pH 1 and practically insoluble above pH 4 in aqueous media.

TAFINLAR (dabrafenib) capsules for oral use are supplied as 50 mg and 75 mg capsules for oral administration. Each 50 mg capsule contains 59.25 mg dabrafenib mesylate equivalent to 50 mg of dabrafenib free base. Each 75 mg capsule contains 88.88 mg dabrafenib mesylate equivalent to 75 mg of dabrafenib free base. The inactive ingredients of TAFINLAR capsules are colloidal silicon dioxide, magnesium stearate, and microcrystalline cellulose. Capsule shells contain hypromellose, red iron oxide (E172), and titanium dioxide (E171).

TAFINLAR (dabrafenib) tablets for oral suspension are supplied as 10 mg tablets for oral administration. Each 10 mg tablet contains 11.85 mg dabrafenib mesylate equivalent to 10 mg of dabrafenib base. The inactive ingredients of TAFINLAR tablets are acesulfame potassium, artificial berry flavor, colloidal silicon dioxide, crospovidone, hypromellose, magnesium stearate, mannitol, microcrystalline cellulose.

12 CLINICAL PHARMACOLOGY

12.1 Mechanism of Action

Dabrafenib is an inhibitor of some mutated forms of BRAF kinases with in vitro IC50 values of 0.65, 0.5, and 1.84 nM for BRAF V600E, BRAF V600K, and BRAF V600D enzymes, respectively. Dabrafenib also inhibits wild-type BRAF and CRAF kinases with IC50 values of 3.2 and 5.0 nM, respectively, and other kinases, such as SIK1, NEK11, and LIMK1 at higher concentrations. Some mutations in the BRAF gene, including those that result in BRAF V600E, can result in constitutively activated BRAF kinases that may stimulate tumor cell growth [see Indications and Usage (1)]. Dabrafenib inhibits cell growth of various BRAF V600 mutation-positive tumors in vitro and in vivo.

Dabrafenib and trametinib target two different kinases in the RAS/RAF/MEK/ERK pathway. Use of dabrafenib and trametinib in combination resulted in greater growth inhibition of BRAF V600 mutation-positive tumor cell lines in vitro and prolonged inhibition of tumor growth in BRAF V600 mutation-positive tumor xenografts compared with either drug alone.

In the setting of BRAF-mutant colorectal cancer, induction of EGFR-mediated MAPK pathway re-activation has been identified as a mechanism of intrinsic resistance to BRAF inhibitors [see Indications and Usage (1.8)].

12.2 Pharmacodynamics

Cardiac Electrophysiology

The potential effect of TAFINLAR on QT interval was assessed in a dedicated multiple-dose study in 32 patients with BRAF V600 mutation-positive tumors. No large changes in the mean QT interval (i.e., > 20 ms) were detected with dabrafenib 300 mg administered twice daily (two times the recommended dosage).

In clinical trials, QTc (heart rate-corrected QT) prolongation to ≥ 500 ms occurred in 0.8% of 264 patients who received TAFINLAR with trametinib and in 1.5% of patients who received TAFINLAR as a single agent. The QTc was increased > 60 ms from baseline in 3.8% of patients who received TAFINLAR with trametinib and 3% of patients treated with TAFINLAR as a single agent.

12.3 Pharmacokinetics

Following administration of TAFINLAR capsules, dabrafenib Cmax and AUC increased in a dose-proportional manner across the dose range of 12 mg (0.08 times the approved recommended adult dose) to 300 mg (2 times the approved recommended adult dose), but the increase was less than dose-proportional after steady state twice-daily dosing. After twice-daily dosing, the mean accumulation ratio was 0.7, and the intersubject variability (CV%) of AUC at steady-state was 38%.

Absorption

The median time to achieve peak plasma concentration (Tmax) is 2 hours. Mean absolute bioavailability of TAFINLAR capsules is 95% and TAFINLAR tablets for oral suspension is 76%.

Effect of Food

Following administration of TAFINLAR capsules, a high-fat meal (approximately 1000 calories, 58-75 grams fat, 58 grams carbohydrates, and 33 grams protein) decreased Cmax by 51%, decreased AUC by 31%, and delayed median Tmax by 3.6 hours as compared with the fasted state.

Administration of a single 150 mg dose of TAFINLAR tablets for the oral suspension with a low-fat, low-calorie meal (approximately 500 calories, 14 grams fat, 80 grams carbohydrates, and 12 grams protein) decreased dabrafenib Cmax by 35% and AUC by 29% as compared with the fasted state.

Distribution

Dabrafenib is 99.7% bound to human plasma proteins. The apparent volume of distribution (Vc/F) is 70.3 L.

Elimination

The mean terminal half-life is 8 hours. Hydroxy-dabrafenib terminal half-life (10 hours) parallels that of dabrafenib while the carboxy- and desmethyl-dabrafenib metabolites exhibit longer half-lives (21 to 22 hours). The apparent clearance of dabrafenib is 17 L/h after a single dose and 34 L/h after twice-daily dosing for 2 weeks.

Metabolism

The metabolism of dabrafenib is primarily mediated by CYP2C8 and CYP3A4 to form hydroxy-dabrafenib. Hydroxy-dabrafenib is further oxidized via CYP3A4 to form carboxy-dabrafenib and subsequently excreted in bile and urine. Carboxy-dabrafenib is decarboxylated to form desmethyl-dabrafenib; desmethyl-dabrafenib may be reabsorbed from the gut. Desmethyl-dabrafenib is further metabolized by CYP3A4 to oxidative metabolites. Mean metabolite-to-parent AUC ratios following repeat-dose administration are 0.9, 11, and 0.7 for hydroxy-, carboxy-, and desmethyl-dabrafenib, respectively. Based on systemic exposure, relative potency, and pharmacokinetic properties, both hydroxy- and desmethyl-dabrafenib are likely to contribute to the clinical activity of dabrafenib.

Excretion

Fecal excretion is the major route of elimination accounting for 71% of radioactive dose while urinary excretion accounted for 23% of total radioactivity as metabolites only.

Specific Populations

Age (18 to 93 years), sex, weight (36 to 170 kg), and renal impairment (eGFR 15 to 89 mL/min/1.73 m^2) have no clinically relevant effect on the pharmacokinetics of dabrafenib.

Pediatric Patients

The pharmacokinetics of dabrafenib in glioma and other solid tumors were evaluated in 243 patients aged 1 to < 18 years following a single dose or multiple doses. Pharmacokinetic parameters in patients aged 1 to < 18 years are within range of values previously observed in adults given the same dose based on weight. Weight (6 to 156 kg) had a statistically significant effect on dabrafenib oral clearance in this population.

Patients with Hepatic Impairment

Mild hepatic impairment (bilirubin ≤ ULN and AST > ULN or bilirubin > 1x to 1.5x ULN and any AST) has no effect on systemic exposure to dabrafenib and its metabolites. No data are available in patients with moderate (bilirubin > 1.5x to 3x ULN and any AST) or severe (bilirubin > 3x to 10x ULN and any AST) hepatic impairment.

Drug Interaction Studies

Effect of Trametinib on Dabrafenib: Coadministration of TAFINLAR 75 mg twice daily with trametinib 2 mg daily resulted in a 23% increase in AUC of dabrafenib, a 33% increase in AUC of desmethyl-dabrafenib, and no change in AUC of hydroxy-dabrafenib as compared with administration of dabrafenib.

Effect of Strong Inhibitors of CYP3A4 or CYP2C8 on Dabrafenib: Coadministration of TAFINLAR 75 mg twice daily and ketoconazole (a strong CYP3A4 inhibitor) for 4 days increased dabrafenib AUC by 71%, hydroxy-dabrafenib AUC by 82%, and desmethyl-dabrafenib AUC by 68%.

Coadministration of TAFINLAR 75 mg twice daily and gemfibrozil (a strong CYP2C8 inhibitor) for 4 days increased dabrafenib AUC by 47%, with no change in the AUC of dabrafenib metabolites.

Effect of Strong Inducers of CYP3A4 or Moderate Inducers of CYP2C8 on Dabrafenib: Coadministration of TAFINLAR 150 mg twice daily and rifampin (a strong CYP3A4 and moderate CYP2C8 inducer) for 10 days decreased dabrafenib AUC by 34% and desmethyl-dabrafenib AUC by 30%, and had no effect on hydroxy-dabrafenib AUC.

Effect of Acid Reducing Agents on Dabrafenib: Coadministration of TAFINLAR 150 mg twice daily and rabeprazole for 4 days did not result in clinically relevant changes in exposures to dabrafenib and its metabolites.

Effect of Dabrafenib on CYP Substrates: Coadministration of TAFINLAR 150 mg twice daily for 15 days and a single dose of midazolam (a CYP3A4 substrate) decreased midazolam AUC by 65%. Coadministration of TAFINLAR 150 mg twice daily for 15 days and a single dose of warfarin decreased the AUC of S-warfarin (a CYP2C9 substrate) by 37% and the AUC of R-warfarin (CYP3A4/CYP1A2 substrate) by 33%.

In vitro data demonstrate that dabrafenib is an inducer of CYP3A4 and CYP2B6 via activation of the pregnane X receptor (PXR) and constitutive androstane receptor (CAR) nuclear receptors. Dabrafenib may also induce CYP2C enzymes via the same mechanism.

Effect of Transporters on Dabrafenib: Dabrafenib and its metabolites, hydroxyl-dabrafenib and desmethyl-dabrafenib, are substrates of human P-glycoprotein (P-gp) and breast cancer resistance protein (BCRP) but are not substrates of organic cation transporter (OCT1) or organic anion transporting polypeptide (OATP1A2, OATP1B1, OATP1B3, OATP2B1) in vitro.

Effect of Dabrafenib on Transporters: Coadministration of TAFINLAR 150 mg twice daily with a single dose of rosuvastatin (a sensitive OATP1B1 and OATP1B3 substrate) increased rosuvastatin Cmax by 2.6-fold but did not change its AUC.

Dabrafenib and its metabolites, hydroxy-dabrafenib, carboxy-dabrafenib, and desmethyl-dabrafenib, are inhibitors of organic anion transporter (OAT1 and OAT3) in vitro. Dabrafenib and desmethyl-dabrafenib are inhibitors of OCT2 and BCRP in vitro.

13 NONCLINICAL TOXICOLOGY

13.1 Carcinogenesis, Mutagenesis, Impairment of Fertility

Carcinogenicity studies with dabrafenib have not been conducted. TAFINLAR increased the risk of cuSCCs in patients in clinical trials.

Dabrafenib was not mutagenic in vitro in the bacterial reverse mutation assay (Ames test) or the mouse lymphoma assay and was not clastogenic in an in vivo rat bone marrow micronucleus test.

In a combined female fertility and embryo-fetal development study in rats, a reduction in fertility was noted at doses greater than or equal to 20 mg/kg/day (equivalent to the human exposure at the recommended adult dose based on AUC). A reduction in the number of ovarian corpora lutea was noted in pregnant females at 300 mg/kg/day (which is approximately three times the human exposure at the recommended adult dose based on AUC).

Male fertility studies with dabrafenib have not been conducted; however, in repeat-dose studies, testicular degeneration/depletion was seen in rats and dogs at doses equivalent to and three times the human exposure at the recommended adult dose based on AUC, respectively.

13.2 Animal Toxicology and/or Pharmacology

Adverse cardiovascular effects were noted in dogs at dabrafenib doses of 50 mg/kg/day (approximately five times the human exposure at the recommended adult dose based on AUC) or greater, when administered for up to 4 weeks. Adverse effects consisted of coronary arterial degeneration/necrosis and hemorrhage, as well as cardiac atrioventricular valve hypertrophy/hemorrhage.

14 CLINICAL STUDIES

14.1 BRAF V600E Mutation-Positive Unresectable or Metastatic Melanoma – TAFINLAR as a Single Agent

BREAK-3 Study

The safety and efficacy of TAFINLAR as a single agent were evaluated in an international, multi-center, randomized (3:1), open-label, active-controlled trial (the BREAK-3 study; NCT01227889) conducted in 250 patients with previously untreated BRAF V600E mutation-positive, unresectable or metastatic melanoma. Patients with any prior use of BRAF inhibitors or MEK inhibitors were excluded. Patients were randomized to receive TAFINLAR 150 mg orally twice daily (n = 187) or dacarbazine 1000 mg/m^2 intravenously every 3 weeks (n = 63). Randomization was stratified by disease stage at baseline [unresectable Stage III (regional nodal or in-transit metastases), M1a (distant skin, subcutaneous, or nodal metastases), or M1b (lung metastases) versus M1c melanoma (all other visceral metastases or elevated serum LDH)]. The main efficacy outcome measure was progression-free survival (PFS) as assessed by the investigator. In addition, an independent radiology review committee (IRRC) assessed the following efficacy outcome measures in pre-specified supportive analyses: PFS, confirmed overall response rate (ORR), and duration of response (DoR).

The median age of patients in the BREAK-3 study was 52 years. The majority of the trial population was male (60%), White (99%), had an ECOG performance status of 0 (67%), had M1c disease (66%), and had normal LDH (62%). All patients had tumor tissue with mutations in BRAF V600E as determined by a clinical trial assay at a centralized testing site. Tumor samples from 243 patients (97%) were tested retrospectively using an FDA-approved companion diagnostic test, tHxID™-BRAF assay.

The median durations of follow-up prior to initiation of alternative treatment in patients randomized to receive TAFINLAR was 5.1 months and in the dacarbazine arm was 3.5 months. Twenty-eight (44%) patients crossed over from the dacarbazine arm at the time of disease progression to receive TAFINLAR.

The BREAK-3 study demonstrated a statistically significant increase in PFS in the patients treated with TAFINLAR. Table 20 and Figure 1 summarize the PFS results.

Table 20. Investigator-Assessed Progression-Free Survival and Confirmed Overall Response Results in the BREAK-3 Study
Investigator-Assessed Endpoints | TAFINLAR N = 187 | Dacarbazine N = 63
Progression-Free Survival
Number of events (%) | 78 (42%) | 41 (65%)
Progressive disease | 76 | 41
Death | 2 | 0
Median, months (95% CI) | 5.1 (4.9, 6.9) | 2.7 (1.5, 3.2)
HRa (95% CI) | 0.33 (0.20, 0.54)
P valueb | < 0.0001
Confirmed Tumor Responses
Overall response rate (95% CI) | 52% (44%, 59%) | 17% (9%, 29%)
Complete response, n (%) | 6 (3%) | 0
Partial response, n (%) | 91 (48%) | 11 (17%)
Duration of response
Median DoR, months (95% CI) | 5.6 (5.4, NR) | NR (5.0, NR)
Abbreviations: CI, confidence interval; DoR, duration of response; HR, hazard ratio; NR, not reached.
a Pike estimator, stratified by disease state.
b Stratified log-rank test.

Figure 1. Kaplan-Meier Curves of Investigator-Assessed Progression-Free Survival in the BREAK-3 Study

In supportive analyses based on IRRC assessment and in an exploratory subgroup analysis of patients with retrospectively confirmed V600E mutation-positive melanoma with the tHxID™-BRAF assay, the PFS results were consistent with those of the primary efficacy analysis.

BREAK-MB Study

The activity of TAFINLAR for the treatment of BRAF V600E mutation-positive melanoma, metastatic to the brain was evaluated in a single-arm, open-label, two-cohort multi-center trial (the BREAK-MB study; NCT01266967). All patients received TAFINLAR 150 mg twice daily. Patients in Cohort A (n = 74) had received no prior local therapy for brain metastases, while patients in Cohort B (n = 65) had received at least one local therapy for brain metastases, including, but not limited to, surgical resection, whole brain radiotherapy, or stereotactic radiosurgery, such as gamma knife, linear-accelerated-based radiosurgery, or charged particles. In addition, patients in Cohort B were required to have evidence of disease progression in a previously treated lesion or an untreated lesion. Additional eligibility criteria were at least one measurable lesion of 0.5 cm or greater in largest diameter on contrast-enhanced MRI, stable or decreasing corticosteroid dose, and no more than two prior systemic regimens for treatment of metastatic disease. The major efficacy outcome measure was estimation of the overall intracranial response rate (OIRR) in each cohort.

The median age of patients in Cohort A was 50 years, 72% were male, 100% were White, 59% had a pre-treatment ECOG performance status of 0, and 57% had elevated LDH at baseline. The median age of patients in Cohort B was 51 years, 63% were male, 98% were White, 66% had a pre-treatment ECOG performance status of 0, and 54% had elevated LDH at baseline. The intracranial response rate as determined by an independent radiology review committee, masked to investigator response assessments, was 18% (95% CI: 10%, 28%) in Cohort A and 18% (95% CI: 10%, 30%) in Cohort B. The median duration of intracranial response was 4.6 months in both cohorts.

14.2 BRAF V600E or V600K Unresectable or Metastatic Melanoma – TAFINLAR With Trametinib

COMBI-d Study and COMBI-v Study

The safety and efficacy of TAFINLAR administered with trametinib were evaluated in two international, randomized, active-controlled trials: one double-blind trial (the COMBI-d study; NCT01584648) and one open-label trial (the COMBI-v study; NCT01597908).

The COMBI-d study compared TAFINLAR plus trametinib to TAFINLAR plus placebo as first-line therapy for patients with unresectable (Stage IIIC) or metastatic (Stage IV) BRAF V600E or V600K mutation-positive cutaneous melanoma. Patients were randomized (1:1) to receive TAFINLAR 150 mg twice daily plus trametinib 2 mg once daily or TAFINLAR 150 mg twice daily plus matching placebo. Randomization was stratified by LDH level (> ULN vs. ≤ ULN) and BRAF mutation subtype (V600E vs. V600K). The major efficacy outcome measure was investigator-assessed progression-free survival (PFS) per RECIST v1.1 with additional efficacy outcome measures of overall survival (OS) and confirmed overall response rate (ORR).

The COMBI-v study compared TAFINLAR and trametinib to vemurafenib as first-line treatment therapy for patients with unresectable (Stage IIIC) or metastatic (Stage IV) BRAF V600E or V600K mutation-positive cutaneous melanoma. Patients were randomized (1:1) to receive TAFINLAR 150 mg twice daily and trametinib 2 mg once daily or vemurafenib 960 mg twice daily. Randomization was stratified by lactate dehydrogenase (LDH) level (> ULN vs. ≤ ULN) and BRAF mutation subtype (V600E vs. V600K). The major efficacy outcome measure was OS. Additional efficacy outcome measures were PFS and ORR as assessed by investigator per RECIST v1.1.

In the COMBI-d study, 423 patients were randomized to TAFINLAR plus trametinib (n = 211) or TAFINLAR plus placebo (n = 212). The median age was 56 years (range: 22 to 89), 53% were male, > 99% were White, 72% had ECOG performance status of 0, 4% had Stage IIIC, 66% had M1c disease, 65% had normal LDH, and 2 patients had a history of brain metastases. All patients had tumor containing BRAF V600E or V600K mutations as determined by centralized testing with the FDA-approved companion diagnostic test; 85% with BRAF V600E mutation positive melanoma and 15% with BRAF V600K mutation positive melanoma.

In the COMBI-v study, 704 patients were randomized to TAFINLAR plus trametinib (n = 352) or single-agent vemurafenib (n = 352). The median age was 55 years (range: 18 to 91), 96% were White, 55% were male, 6% had Stage IIIC, 61% had M1c disease, 67% had normal LDH, 70% had ECOG performance status of 0, 89% had BRAF V600E mutation-positive melanoma, and one patient had a history of brain metastases.

The COMBI-d and COMBI-v studies demonstrated statistically significant improvements in OS and PFS. Table 21 and Figures 2 and 3 summarize the efficacy results.

Table 21. Efficacy Results in Patients with BRAF V600E or V600K Mutation-Positive Unresectable or Metastatic Melanomaa
Endpoint | COMBI-d Study |  | COMBI-v Study
 | TAFINLAR plus Trametinib N = 211 | TAFINLAR plus Placebo N = 212 | TAFINLAR plus Trametinib N = 352 | Vemurafenib N = 352
Overall Survival
Number of deaths (%) | 99 (47%) | 123 (58%) | 100 (28%) | 122 (35%)
Median, months (95% CI) | 25.1 (19.2, NR) | 18.7 (15.2, 23.1) | NR (18.3, NR) | 17.2 (16.4, NR)
HR (95% CI) | 0.71 (0.55, 0.92) |  | 0.69 (0.53, 0.89)
P value (log-rank test) | 0.01 |  | 0.005a
Progression-Free Survivalb
Number of events (%) | 102 (48%) | 109 (51%) | 166 (47%) | 217 (62%)
Median, months (95% CI) | 9.3 (7.7, 11.1) | 8.8 (5.9, 10.9) | 11.4 (9.9, 14.9) | 7.3 (5.8, 7.8)
HR (95% CI) | 0.75 (0.57, 0.99) |  | 0.56 (0.46, 0.69)
P value (log-rank test) | 0.035 |  | < 0.001
Overall Response Rateb
ORR (95% CI) | 66% (60%, 73%) | 51% (44%, 58%) | 64% (59%, 69%) | 51% (46%, 56%)
P value | < 0.001 |  | < 0.001
Complete response | 10% | 8% | 13% | 8%
Partial response | 56% | 42% | 51% | 43%
Median DoR, months (95% CI) | 9.2 (7.4, NR) | 10.2 (7.5, NR) | 13.8 (11.0, NR) | 7.5 (7.3, 9.3)
Abbreviations: CI, confidence interval; DoR, duration of response; HR, hazard ratio; NR, not reached; ORR, overall response rate.
a P-value is comparing with the allocated alpha of 0.021 for the interim analysis based on 77% information.
b PFS and ORR were assessed by investigator.

Figure 2. Kaplan-Meier Curves for Overall Survival in the COMBI-d Study
Figure 3. Kaplan-Meier Curves for Overall Survival in the COMBI-v Study

COMBI-MB Study

The activity of TAFINLAR with trametinib for the treatment of BRAF V600E or V600K mutation-positive melanoma, metastatic to the brain, was evaluated in a non-randomized, open-label, multi-center, multi-cohort trial (the COMBI-MB study; NCT02039947). Eligible patients were required to have at least one measurable intracranial lesion and to have no leptomeningeal disease, parenchymal brain metastasis greater than 4 cm in diameter, ocular melanoma, or primary mucosal melanoma. Patients received TAFINLAR 150 mg orally twice daily and trametinib 2 mg orally once daily until disease progression or unacceptable toxicity. The major efficacy outcome measure was intracranial response rate, defined as the percentage of patients with a confirmed intracranial response per RECIST v1.1, modified to allow up to five intracranial target lesions at least 5 mm in diameter, as assessed by independent review.

The COMBI-MB study enrolled 121 patients with a BRAF V600E (85%) or V600K (15%) mutation. The median age was 54 years (range: 23 to 84), 58% were male, 100% were White, 8% were from the United States, 65% had normal LDH at baseline, and 97% had an ECOG performance status of 0 or 1. Intracranial metastases were asymptomatic in 87% and symptomatic in 13% of patients, 22% received prior local therapy for brain metastases, and 87% also had extracranial metastases.

The intracranial response rate was 50% (95% CI: 41, 60), with a complete response rate of 4.1% and a partial response rate of 46%. The median duration of intracranial response was 6.4 months (range: 1 to 31). Of the patients with an intracranial response, 9% had stable or progressive disease as their best overall response.

14.3 Adjuvant Treatment of BRAF V600E or V600K Mutation-Positive Melanoma

The efficacy of TAFINLAR administered with trametinib was evaluated in an international, multi-center, randomized, double-blind, placebo-controlled trial (COMBI AD; NCT01682083) that enrolled patients with Stage III melanoma with BRAF V600E or V600K mutations as detected by the tHxID™-BRAF assay and pathologic involvement of regional lymph node(s). Enrollment required complete resection of melanoma with complete lymphadenectomy within 12 weeks prior to randomization. The trial excluded patients with mucosal or ocular melanoma, unresectable in-transit metastases, distant metastatic disease, or prior systemic anti-cancer treatment, including radiotherapy. Patients were randomized (1:1) to receive TAFINLAR 150 mg twice daily and trametinib 2 mg once daily or two placebos for up to 1 year. Randomization was stratified by BRAF mutation status (V600E or V600K) and American Joint Committee on Cancer (AJCC; 7th Edition) Stage (IIIA, IIIB, or IIIC). The major efficacy outcome measure was relapse-free survival (RFS), defined as the time from randomization to disease recurrence (local, regional, or distant metastasis), new primary melanoma, or death from any cause, whichever occurred first as assessed by the investigator. Patients underwent imaging for tumor recurrence every 3 months for the first two years and every 6 months thereafter.

In COMBI-AD, a total of 870 patients were randomized: 438 to TAFINLAR in combination with trametinib and 432 to placebo. Median age was 51 years (range: 18 to 89), 55% were male, 99% were White, and 91% had an ECOG performance status of 0. Disease characteristics were AJCC Stage IIIA (18%), Stage IIIB (41%), Stage IIIC (40%), stage unknown (1%); BRAF V600E mutation (91%), BRAF V600K mutation (9%); macroscopic lymph nodes (65%); and tumor ulceration (41%).

The median duration of follow-up at the time of the primary analysis was 2.8 years.

COMBI-AD showed a statistically significant improvement in RFS in patients randomized to TAFINLAR in combination with trametinib compared to those randomized to placebo. Efficacy results are presented in Table 22 and Figure 4.

Table 22. Efficacy Results in COMBI-AD in the Adjuvant Treatment of Melanoma
Investigator-Assessed Endpoint | TAFINLAR plus Trametinib N = 438 | Placebo N = 432
Relapse-Free Survival
Number of events (%) | 166 (38) | 248 (57)
Median, months (95% CI) | NE (44.5, NE) | 16.6 (12.7, 22.1)
HR (95% CI)a | 0.47 (0.39, 0.58)
P valueb | < 0.0001
Abbreviations: CI, confidence interval; HR, hazard ratio; NE, not estimable.
aPike estimator obtained from the stratified log-rank test.
bLog-rank test stratified by disease stage (IIIA vs. IIIB vs. IIIC) and BRAF V600 mutation type (V600E vs. V600K).

Figure 4. Kaplan-Meier Curves for Investigator-Assessed Relapse-Free Survival in COMBI-AD in the Adjuvant Treatment of Melanoma

The median duration of follow-up at the time of the final overall survival analysis was 8.0 years. The estimated hazard ratio for overall survival was 0.80 (95% CI: 0.62, 1.01; p = 0.063) with 125 events (29%) in the combination arm and 136 events (31%) in the placebo arm. Median overall survival was not estimable in both arms.

14.4 BRAF V600E Mutation-Positive Metastatic Non-Small Cell Lung Cancer

The safety and efficacy of TAFINLAR alone or administered with trametinib were evaluated in a multi-center, three-cohort, non-randomized, activity-estimating, open-label trial (Study BRF113928, NCT01336634). Key eligibility criteria were locally confirmed BRAF V600E mutation-positive metastatic NSCLC, no prior exposure to BRAF or MEK-inhibitor, and absence of EGFR mutation or ALK rearrangement (unless patients had progression on prior tyrosine kinase inhibitor therapy). Patients enrolled in Cohorts A and B were required to have received at least one previous platinum-based chemotherapy regimen for NSCLC with demonstrated disease progression but no more than three prior systemic regimens. Patients enrolled in Cohort C could not have received prior systemic therapy for metastatic NSCLC. Patients in Cohort A received TAFINLAR 150 mg twice daily. Patients in Cohorts B and C received TAFINLAR 150 mg twice daily and trametinib 2 mg once daily. The major efficacy outcome measure was overall response rate (ORR) per RECIST v1.1 as assessed by independent review committee (IRC) and duration of response (DoR).

There were a total of 171 patients enrolled which included 78 patients enrolled in Cohort A, 57 patients enrolled in Cohort B, and 36 patients enrolled in Cohort C. The characteristics of the study population were: a median age of 66 years, 48% male; 81% White, 14% Asian, 3% Black, and 2% Hispanic; 60% former smokers, 32% never smokers, and 8% current smokers; 27% had ECOG performance status (PS) of 0, 63% had ECOG PS of 1, and 11% had ECOG PS of 2; 99% had metastatic disease of which 6% had brain metastasis at baseline and 14% had liver metastasis at baseline; 11% had systemic anti-cancer therapy in the adjuvant setting and 58% of the 135 previously treated patients had only one line of prior systemic therapy for metastatic disease; 98% had non-squamous histology.

Efficacy results are summarized in Table 23.

Table 23. Efficacy Results Based on Independent Review in Study BRF113928
Treatment | TAFINLAR | TAFINLAR plus Trametinib
Population | Previously Treated N = 78 | Previously Treated N = 57 | Treatment Naïve N = 36
Overall Response Ratea
ORR (95% CI) | 27% (18%, 38%) | 61% (48%, 74%) | 61% (44%, 77%)
Complete response | 1% | 5% | 8%
Partial response | 26% | 56% | 53%
Duration of Responsea | n = 21 | n = 35 | n = 22
Median DoR, months (95% CI) | 18.0 (4.2, 40.1) | 9.0 (5.8, 26.2) | 15.2 (7.8, 23.5)
Abbreviations: CI, confidence interval; DoR, duration of response; ORR, overall response rate.
a Represents final analysis results (cutoff date of 24 Feb 2021) for the primary analysis responder cohorts.

In a subgroup analysis of patients with retrospectively, centrally confirmed BRAF V600E mutation-positive NSCLC with the Oncomine™ Dx Target Test, the ORR results were similar to those presented in Table 22.

14.5 BRAF V600E Mutation-Positive Locally Advanced or Metastatic Anaplastic Thyroid Cancer

The safety and efficacy of TAFINLAR administered with trametinib was evaluated in an activity-estimating, nine-cohort, multi-center, non-randomized, open-label trial (Study BRF117019; NCT02034110) in patients with rare cancers with the BRAF V600E mutation, including locally advanced, unresectable, or metastatic ATC with no standard locoregional treatment options. Trial BRF117019 excluded patients who could not swallow or retain the medication; who received prior treatment with BRAF or MEK inhibitors; with symptomatic or untreated CNS metastases; or who had airway obstruction. Patients received TAFINLAR 150 mg twice daily and trametinib 2 mg once daily. The major efficacy outcome measure was overall response rate (ORR) per RECIST v1.1 as assessed by independent review committee (IRC) and duration of response (DoR).

Thirty-six patients were enrolled and were evaluable for response in the ATC cohort. The median age was 71 years (range: 47 to 85); 44% were male, 50% White, 44% Asian; and 94% had ECOG performance status of 0 or 1. Prior anti-cancer treatments included surgery and external beam radiotherapy (83% each), and systemic therapy (67%).

Efficacy results are summarized in Table 24.

Table 24. Efficacy Results in the ATC Cohort Based on Independent Review of Study BRF117019
ATC Cohort Population | N = 36
Overall Response Rate
ORR (95% CI) | 53% (35.5%, 69.6%)
Complete response | 6%
Partial response | 47%
Duration of Response | n = 19
Median DoR, months (95% CI) | 13.6 (3.8, NE)
% with DoR ≥ 6 months | 68%
% with DoR ≥ 12 months | 53%
Abbreviations: ATC, anaplastic thyroid cancer; CI, confidence interval; DoR, duration of response; NE, not estimable; ORR, overall response rate.

14.6 BRAF V600E Mutation-Positive Unresectable or Metastatic Solid Tumors

The safety and efficacy of TAFINLAR in combination with trametinib for the treatment of BRAF V600E mutation-positive unresectable or metastatic solid tumors were evaluated in Trials BRF117019, NCI-MATCH, and CTMT212X2101, and supported by results in COMBI-d, COMBI-v [see Clinical Studies (14.2)], and BRF113928 [see Clinical Studies (14.4)]. In adult studies, patients received TAFINLAR 150 mg twice daily and trametinib 2 mg once daily. The major efficacy outcome measures were ORR per RECIST v1.1, RANO [HGG] or modified RANO [LGG] criteria and duration of response (DoR).

BRF117019 Study and NCI-MATCH Study

Study BRF117019 (NCT02034110) [see Clinical Studies (14.5)] is a multi-cohort, multi-center, non-randomized, open-label trial in adult patients with selected tumors with the BRAF V600E mutation, including high-grade glioma (HGG) (n = 45), biliary tract cancer (BTC) (n = 43), low-grade glioma (LGG) (n = 13), adenocarcinoma of small intestine (ASI) (n = 3), gastrointestinal stromal tumor (GIST) (n = 1), and anaplastic thyroid cancer [see Clinical Studies (14.5)]. Patients were enrolled based on local assessments of BRAF V600E mutation status; a central laboratory confirmed the BRAF V600E mutation in 93 of 105 patients.

Arm H (EAY131-H) of the NCI-MATCH study (NCT02465060) is a single-arm, open-label study that enrolled patients with a BRAF V600E mutation. Patients with melanoma, thyroid cancer, or CRC were excluded. BRAF V600E mutation status for enrollment was determined either by central or local laboratory test. The study included adult patients with solid tumors including gastrointestinal tumors (n = 14), lung tumors (n = 7), gynecologic or peritoneal tumors (n = 6), CNS tumors (n = 4), and ameloblastoma of mandible (n = 1).

Among the 131 patients enrolled in BRF117019 and NCI-MATCH with the tumor types shown in Table 25, the baseline characteristics were: median age of 51 years with 20% age 65 or older; 56% female; 85% White, 9% Asian, 3% Black, 3% other; and 37% ECOG PS of 0, 56% ECOG PS of 1, and 6% ECOG PS of 2. Of the 131 patients, 90% received prior systemic therapy.

Efficacy results in patients with solid tumors are summarized in Table 25.

Table 25. Efficacy Results Based on Independent Review in Studies BRF117019 and NCI-MATCH Arm H
Tumor Typea | N | Objective Response Rate |  | Duration of Response
 |  | % | 95% CI | Range (months)
Biliary tract cancerb | 48 | 46 | (31, 61) | 1.8d, 40d
High-grade gliomac | 48 | 33 | (20, 48) | 3.9, 44
Glioblastoma | 32 | 25 | (12, 43) | 3.9, 27
Anaplastic pleomorphic xanthoastrocytoma | 6 | 67 | (22, 96) | 6, 43
Anaplastic astrocytoma | 5 | 20 | (0.5, 72) | 15
Astroblastoma | 2 | 100 | (16, 100) | 15, 23d
Undifferentiated | 1 | PR | (2.5, 100) | 6
Anaplastic ganglioglioma | 1 | 0 | NA | NA
Anaplastic oligodendroglioma | 1 | 0 | NA | NA
Low-grade glioma | 14 | 50 | (23, 77) | 6, 29d
Astrocytoma | 4 | 50 | (7, 93) | 7, 23
Ganglioglioma | 4 | 50 | (7, 93) | 6, 13
Pleomorphic xanthoastrocytoma | 2 | 50 | (1.3, 99) | 6
Pilocytic astrocytoma | 2 | 0 | NA | NA
Choroid plexus papilloma | 1 | PR | (2.5, 100) | 29d
Gangliocytoma/ganglioglioma | 1 | PR | (2.5, 100) | 18d
Low-grade serous ovarian carcinoma | 5 | 80 | (28, 100) | 12, 42d
Adenocarcinoma small intestine | 4 | 50 | (7, 93) | 7, 8
Adenocarcinoma pancreas | 3 | 0 | NA | NA
Mixed ductal/adenoneuroendocrine carcinoma | 2 | 0 | NA | NA
Neuroendocrine carcinoma of colon | 2 | 0 | NA | NA
Ameloblastoma of mandible | 1 | PR | (2.5, 100) | 30
Combined small cell-squamous carcinoma of lung | 1 | PR | (2.5, 100) | 5
Mucinous-papillary serous adenocarcinoma of peritoneum | 1 | PR | (2.5, 100) | 8
Adenocarcinoma of anus | 1 | 0 | NA | NA
Gastrointestinal stromal tumor | 1 | 0 | NA | NA
Abbreviations: NA, not applicable; PR, partial response.
aExcludes NSCLC (n = 6) and ATC (n = 36) (previously approved tumor types for TAFINLAR in combination with trametinib).
bMedian DoR 9.8 months (95% CI: 5.3, 20.4).
cMedian DoR 13.6 months (95% CI: 5.5, 26.7).
dDenotes a right-censored DoR.

CTMT212X2101 (X2101) Study

Study X2101 (NCT02124772) was a multi-center, open-label, multi-cohort study in pediatric patients with refractory or recurrent solid tumors. Part C was a dose escalation of TAFINLAR in combination with trametinib in patients with a BRAF V600E mutation. Part D was a cohort expansion phase of TAFINLAR in combination with trametinib in patients with LGG with a BRAF V600E mutation. The major efficacy outcome measure was ORR as assessed by independent review committee per RANO criteria.

The efficacy of TAFINLAR in combination with trametinib was evaluated in 48 pediatric patients, including 34 patients with LGG and 2 patients with HGG.

For patients with BRAF V600E mutation positive LGG and HGG in Parts C and D, the median age was 10 years (range: 1 to 17); 50% were male, 75% White, 8% Asian, 3% Black; and 58% had Karnofsky/Lansky performance status of 100. Prior anti-cancer treatments included surgery (83%), external beam radiotherapy (2.8%), and systemic therapy (92%). The ORR was 25% (95% CI: 12%, 42%). For the 9 patients who responded, DoR was ≥ 6 months for 78% of patients and ≥ 24 months for 44% of patients.

CDRB436G2201 (G2201) Study – High-Grade Glioma Cohort

Study G2201 (NCT02684058) was a multi-center, randomized, open-label, Phase II study of dabrafenib and trametinib in chemotherapy-naïve pediatric patients with BRAF V600E mutant low-grade glioma (LGG) and patients with relapsed or progressive BRAF V600E mutant HGG. Patients with HGG were enrolled in a single-arm cohort. The major efficacy outcome measure for the HGG cohort was ORR as assessed by independent review committee per RANO 2010 criteria.

The efficacy of TAFINLAR in combination with trametinib was evaluated in 41 pediatric patients with relapsed or progressive HGG.

For patients with BRAF V600E mutant HGG enrolled in the HGG cohort, the median age was 13 years (range: 2 to 17); 56% were female, 61% White, 27% Asian, 2.4% Black, and 37% had Karnofsky/Lansky performance status of 100. Prior anti-cancer treatments included surgery (98%), radiotherapy (90%), and chemotherapy (81%). The ORR was 56% (95% CI: 40, 72). The median DoR was not reached (95% CI: 9.2, NE). For the 23 patients who responded in the HGG cohort, DoR was ≥ 6 months for 78% of patients, ≥ 12 months for 48% of patients, and ≥ 24 months for 22% of patients.

14.7 BRAF V600E Mutation-Positive Low-Grade Glioma

CDRB436G2201 (G2201) Study – Low-Grade Glioma Cohort

The safety and efficacy of TAFINLAR in combination with trametinib for the treatment of BRAF V600E mutation-positive low-grade glioma (LGG) in pediatric patients aged 1 to < 18 years of age were evaluated in the multi-center, open-label trial (Study CDRB436G2201; NCT02684058). Patients with LGG (WHO grades 1 and 2) who required first systemic therapy were randomized in a 2:1 ratio to dabrafenib plus trametinib (D + T) or carboplatin plus vincristine (C + V).

BRAF mutation status was identified prospectively via a local assessment or a central laboratory test. In addition, retrospective testing of available tumor samples by the central laboratory was performed to evaluate BRAF V600E mutation status.

Patients received age- and weight-based dosing of TAFINLAR and trametinib until loss of clinical benefit or until unacceptable toxicity. Carboplatin and vincristine were dosed based on body surface area at doses 175 mg/m^2 and 1.5 mg/m^2 (0.05 mg/kg for patients < 12 kg), respectively, as one 10-week induction course followed by eight 6-week cycles of maintenance therapy.

The major efficacy outcome measure was overall response rate (ORR) by independent review based on RANO LGG (2017) criteria. Additional efficacy outcome measures were progression-free survival and overall survival. The primary analysis was performed when all patients had completed at least 32 weeks of therapy.

In the LGG cohort, 110 patients were randomized to D + T (n = 73) or C + V (n = 37). Median age was 9.5 years (range: 1 to 17); 60% were female. Study G2201 showed a statistically significant improvement in ORR and PFS in LGG patients randomized to D + T compared to those randomized to C + V. Efficacy results are shown in Table 26.

Table 26. Efficacy Results Based on Independent Review in Study G2201 (LGG Cohort)
 | TAFINLAR plus Trametinib N = 73 | Carboplatin plus Vincristine N = 37
Overall Response Rate
ORR% (95% CI)a | 46.6 (34.8, 58.6) | 10.8 (3.0, 25.4)
P-value | < 0.001
Complete response, n (%) | 2 (2.7) | 1 (2.7)
Partial response, n (%) | 32 (44) | 3 (8)
Duration of Response
Median (95% CI)b, months | 23.7 (14.5, NE) | NE (6.6, NE)
% with observed DoR ≥ 12 months | 56 | 50
% with observed DoR ≥ 24 months | 15 | 25
Progression-Free Survival
Median (95% CI)b, months | 20.1 (12.8, NE) | 7.4 (3.6, 11.8)
Hazard ratio (95% CI)c | 0.31 (0.17, 0.55)
P-value | < 0.001
Abbreviations: CI, confidence interval; DoR, duration of response; NE, not estimable; ORR, overall response rate.
a Based on Clopper-Pearson exact confidence interval.
b Based on Kaplan-Meier method.
c Based on proportional hazards model.

Figure 5. Kaplan-Meier Curves for Progression-Free Survival in Study G2201 (LGG Cohort)

At the time of the interim analysis of overall survival (OS), conducted when all patients had completed at least 32 weeks of treatment or had discontinued earlier, there was one death on the C + V arm. The OS results at interim analysis did not reach statistical significance.

16 HOW SUPPLIED/STORAGE AND HANDLING

TAFINLAR Capsules:

50 mg capsules: Dark red capsule imprinted with ‘GS TEW’ and ‘50 mg’ available in bottles of 120 with child-resistant closures (NDC 0078-0682-66). Each bottle contains a silica gel desiccant.

75 mg capsules: Dark pink capsule imprinted with ‘GS LHF’ and ‘75 mg’ available in bottles of 120 with child-resistant closures (NDC 0078-0681-66). Each bottle contains a silica gel desiccant.

Store at 20°C to 25°C (68°F to 77°F); excursions permitted between 15°C and 30°C (59°F and 86°F) [see USP Controlled Room Temperature]. Store and dispense in the original bottle with the desiccant.

TAFINLAR Tablets for Oral Suspension:

10 mg tablets for oral suspension: white to slightly yellow, round biconvex 6 mm tablet debossed with “D” on one side and “NVR” on the other side. Available in bottles of 210 with child-resistant closures (NDC 0078-1154-21). Each bottle contains 2 silica gel desiccants.

Store at 20°C to 25°C (68°F to 77°F); excursions permitted between 15°C and 30°C (59°F and 86°F) [see USP Controlled Room Temperature]. Store and dispense in the original bottle with the desiccant.

17 PATIENT COUNSELING INFORMATION

Advise the patient to read the FDA-approved patient labeling (Medication Guide and Instructions for Use).

New Primary Cutaneous and Non-Cutaneous Malignancies

Advise patients that TAFINLAR increases the risk of developing new primary cutaneous and non-cutaneous malignancies. Advise patients to contact their healthcare provider immediately for any new lesions, changes to existing lesions on their skin, or signs and symptoms of other malignancies [see Warnings and Precautions (5.1)].

Hemorrhage

Advise patients that TAFINLAR administered with trametinib increases the risk of intracranial and gastrointestinal hemorrhage. Advise patients to contact their healthcare provider to seek immediate medical attention for signs or symptoms of unusual bleeding or hemorrhage [see Warnings and Precautions (5.3)].

Cardiomyopathy

Advise patients that TAFINLAR can cause cardiomyopathy and to immediately report any signs or symptoms of heart failure to their healthcare provider [see Warnings and Precautions (5.4)].

Uveitis

Advise patients that TAFINLAR can cause uveitis, including iritis and iridocyclitis and to contact their healthcare provider if they experience any changes in their vision [see Warnings and Precautions (5.5)].

Serious Febrile Reactions

Advise patients that TAFINLAR can cause pyrexia, including serious febrile reactions. Inform patients that the incidence and severity of pyrexia are increased when TAFINLAR is administered with trametinib. Instruct patients to contact their healthcare provider if they develop a fever while taking TAFINLAR [see Warnings and Precautions (5.6)].

Serious Skin Toxicities

Advise patients that TAFINLAR can cause serious skin toxicities and to contact their healthcare provider for progressive or intolerable rash. Advise patients to contact their healthcare provider immediately if they develop signs and symptoms of a severe skin reaction [see Warnings and Precautions (5.7)].

Hyperglycemia

Advise patients that TAFINLAR can impair glucose control in diabetic patients resulting in the need for more intensive hypoglycemic treatment and to contact their healthcare provider to report symptoms of severe hyperglycemia [see Warnings and Precautions (5.8)].

Glucose-6-phosphate Dehydrogenase (G6PD) Deficiency

Advise patients that TAFINLAR may cause hemolytic anemia in patients with G6PD deficiency. Advise patients with known G6PD deficiency to contact their healthcare provider to report signs or symptoms of anemia or hemolysis [see Warnings and Precautions (5.9)].

Embryo-Fetal Toxicity

- Advise pregnant women and females of reproductive potential of the potential risk to a fetus [see Warnings and Precautions (5.12), Use in Specific Populations (8.1, 8.3)].
- Advise females to contact their healthcare provider of a known or suspected pregnancy.
- Advise females of reproductive potential to use effective non-hormonal contraception during treatment and for 2 weeks after discontinuation of treatment with TAFINLAR.
- Advise male patients with female partners of reproductive potential to use condoms during treatment with TAFINLAR and for 2 weeks after the last dose.

Lactation

Advise women not to breastfeed during treatment with TAFINLAR and for 2 weeks after the last dose of TAFINLAR [see Use in Specific Populations (8.2)].

Infertility

Advise males and females of reproductive potential of the potential risk for impaired fertility with TAFINLAR [see Use in Specific Populations (8.3)].

Administration

- Instruct patients to take TAFINLAR capsules on an empty stomach (at least 1 hour before or 2 hours after a meal) [see Dosage and Administration (2.3)].
- Instruct patients to take the oral suspension on an empty stomach (at least 1 hour before or 2 hours after a meal). Breastfeeding and/or baby formula may be given on demand if a pediatric patient is unable to tolerate the fasting conditions [see Dosage and Administration (2.3)].

tHxID™ is a trademark of bioMérieux.

Oncomine™ Dx Target Test is a trademark of Life Technologies Corporation, a part of Thermo Fisher Scientific Inc.

Distributed by:
Novartis Pharmaceuticals Corporation
East Hanover, New Jersey 07936

© Novartis

T2025-26

MEDICATION GUIDE

TAFINLAR® (TAFF-in-lar)
(dabrafenib)
capsules

TAFINLAR® (TAFF-in-lar)
(dabrafenib)
tablets for oral suspension

Important information: If your healthcare provider prescribes TAFINLAR for you to be taken or given with trametinib, also read the Patient Information leaflet that comes with trametinib.

What is the most important information I should know about TAFINLAR?
TAFINLAR may cause serious side effects, including:
Risk of new cancers. TAFINLAR, when used alone or with trametinib, may cause skin cancers, called cutaneous squamous cell carcinoma (cuSCC), keratoacanthoma, basal cell carcinoma, or melanoma.
Talk with your healthcare provider about your risk for these cancers.
Check your skin and tell your healthcare provider right away about any skin changes, including a:

- new wart
- skin sore or reddish bump that bleeds or does not heal
- change in size or color of a mole

Your healthcare provider should check your skin before treatment with TAFINLAR, every 2 months during treatment with TAFINLAR, and for up to 6 months after you stop taking TAFINLAR to look for any new skin cancers.
Your healthcare provider should also check for cancers that may not occur on the skin. Tell your healthcare provider about any new symptoms that develop during treatment with TAFINLAR.
See "What are the possible side effects of TAFINLAR?" for more information about side effects.

What is TAFINLAR?
TAFINLAR is a prescription medicine used:

- alone or in combination with a medicine called trametinib to treat a type of skin cancer called melanoma:
  ○ that has spread to other parts of the body or cannot be removed by surgery, and
  ○ that has a certain type of abnormal “BRAF” gene.
- in combination with trametinib, to help prevent melanoma that has a certain type of abnormal “BRAF” gene from coming back after the cancer has been removed by surgery.
- in combination with trametinib to treat a type of lung cancer called non-small cell lung cancer (NSCLC):
  ○ that has spread to other parts of the body, and
  ○ that has a certain type of abnormal “BRAF” gene.
- in combination with trametinib to treat a type of thyroid cancer called anaplastic thyroid cancer (ATC):
  ○ that has spread to other parts of the body and you have no satisfactory treatment options, and
  ○ that has a certain type of abnormal “BRAF” gene.
- in combination with trametinib to treat solid tumors in adults and children 1 year and older:
  ○ that cannot be removed with surgery or have spread to other parts of the body, and that have gotten worse (progressed), and you have no satisfactory treatment options, and
  ○ that have a certain type of abnormal “BRAF” gene.
- in combination with trametinib to treat a type of brain tumor called glioma in children 1 year and older:
  ○ that is low-grade glioma (LGG), and
  ○ that have a certain type of abnormal “BRAF” gene, and
  ○ who require a medicine by mouth or injection (systemic therapy).

TAFINLAR is not for use in treating people with colorectal cancer or wild-type BRAF solid tumors.
Your healthcare provider will perform a test to make sure that TAFINLAR is right for you.
It is not known if TAFINLAR used in combination with trametinib is safe and effective in children less than 1 year of age.
It is not known if TAFINLAR used alone is safe and effective in children.

Before you take or give TAFINLAR, tell your healthcare provider about all of your medical conditions, including if you:

- have had bleeding problems
- have heart problems
- have eye problems
- have liver or kidney problems
- have diabetes
- plan to have surgery, dental, or other medical procedures
- have a deficiency of the glucose-6-phosphate dehydrogenase (G6PD) enzyme
- are pregnant or plan to become pregnant. TAFINLAR can harm your unborn baby.
  Females who are able to become pregnant:
  ○ Your healthcare provider will do a test to see if you are pregnant before starting treatment with TAFINLAR.
  ○ You should use effective non-hormonal birth control (contraception) during treatment with TAFINLAR and for 2 weeks after your last dose of TAFINLAR.
  ○ Birth control methods that contain hormones (such as birth control pills, injections, or transdermal systems) may not work as well during treatment with TAFINLAR and you could become pregnant. You should use another effective method of birth control during treatment with TAFINLAR.
  ○ Talk to your healthcare provider about birth control methods that may be right for you during this time.
  ○ Tell your healthcare provider right away if you become pregnant or think you might be pregnant during treatment with TAFINLAR.
  Males (including those who have had a vasectomy) with a female partner who is able to become pregnant:
  ○ Use condoms during sexual intercourse during treatment with TAFINLAR and for at least 2 weeks after your last dose of TAFINLAR.
- are breastfeeding or plan to breastfeed. It is not known if TAFINLAR passes into your breast milk. Do not breastfeed during treatment and for 2 weeks after your last dose of TAFINLAR. Talk to your healthcare provider about the best way to feed your baby during this time.

Tell your healthcare provider about all the medicines you take, including prescription and over-the-counter medicines, vitamins, and herbal supplements.
Taking TAFINLAR with certain other medicines may affect the way TAFINLAR and the other medicines work and may increase your risk of side effects. Know the medicines you take. Keep a list of them to show your healthcare provider and pharmacist when you get a new medicine.

How should I take or give TAFINLAR?

- Take or give TAFINLAR exactly as your healthcare provider tells you. Do not change your dose or stop TAFINLAR unless your healthcare provider tells you.
- Your healthcare provider may change your dose of TAFINLAR, temporarily stop, or completely stop your treatment with TAFINLAR if you develop certain side effects.
- If you miss a dose of TAFINLAR, take or give it as soon as you remember. Do not take or give a missed dose of TAFINLAR if it is less than 6 hours before your next scheduled dose. Just skip the missed dose and take or give the next dose of TAFINLAR at the regular time.
- If vomiting happens after taking or giving a dose of TAFINLAR, do not take or give an additional dose. Take or give the next dose of TAFINLAR at the regular time.

TAFINLAR capsules:

- Take TAFINLAR 2 times a day, at the same time each day, about 12 hours apart.
- Take TAFINLAR on an empty stomach (at least 1 hour before or 2 hours after a meal).
- Take TAFINLAR capsules whole. Do not open, crush, or break TAFINLAR capsules.
- If TAFINLAR capsules are prescribed for your child weighing at least 57 pounds (26 kg), your child’s healthcare provider will adjust their dose as your child grows.
- Tell your healthcare provider if you or your child is not able to swallow TAFINLAR capsules whole.

TAFINLAR tablets for oral suspension:

- If TAFINLAR tablets for oral suspension are prescribed for your child, your child’s healthcare provider will adjust their dose as your child grows.
- TAFINLAR tablets for oral suspension are to be taken or given as a suspension only.
- Do not swallow whole, chew or crush TAFINLAR tablets for oral suspension.
- See the “Instructions for Use” that comes with the medicine for instructions on how to correctly prepare and take or give a dose of the TAFINLAR oral suspension.
- After the TAFINLAR tablets for oral suspension are dispersed into an oral suspension, take or give the medicine right away from a dosing cup, oral syringe or feeding tube (10 French gauge or larger for 1 to 3 tablets, 12 French gauge or larger for 4 to 15 tablets).
- Take or give TAFINLAR oral suspension 2 times a day, at the same time each day, about 12 hours apart.
- Take or give each dose of TAFINLAR oral suspension on an empty stomach (at least 1 hour before or 2 hours after a meal). If necessary, breastfeeding or baby formula may be given on demand.
- Throw away (dispose of) the prepared TAFINLAR oral suspension if it is not used within 30 minutes.

What are the possible side effects of TAFINLAR?
TAFINLAR may cause serious side effects, including:

- See “What is the most important information I should know about TAFINLAR?”
- bleeding problems. TAFINLAR, when taken or given with trametinib, can cause serious bleeding problems, especially in your brain or stomach, that can lead to death. Call your healthcare provider and get medical help right away if you have any signs of bleeding, including:
  ○ headaches, dizziness, or feeling weak
  ○ cough up blood or blood clots
  ○ vomit blood or your vomit looks like “coffee grounds”
  ○ red or black stool that looks like tar
- heart problems, including heart failure. Your healthcare provider should check your heart function before and during treatment with TAFINLAR. Call your healthcare provider right away if you have any of the following signs and symptoms of a heart problem:
  ○ feeling like your heart is pounding, racing, or beating irregularly
  ○ shortness of breath
  ○ swelling of your ankles or feet
  ○ feeling lightheaded
- eye problems. TAFINLAR can cause severe eye problems that can lead to blindness. Call your healthcare provider right away if you get these symptoms of eye problems:
  ○ blurred vision, loss of vision, or other vision changes
  ○ see color dots
  ○ halo (see blurred outline around objects)
  ○ eye pain, swelling, or redness
- fever. Fever is common during treatment with TAFINLAR, but may also be serious. When taking TAFINLAR with trametinib, fever may happen more often or may be more severe. In some cases, chills or shaking chills, too much fluid loss (dehydration), low blood pressure, dizziness, or kidney problems may happen with the fever.
  Call your healthcare provider right away if you get a fever during treatment with TAFINLAR.
  Your healthcare provider may temporarily or permanently stop your treatment or change your dose of TAFINLAR with trametinib if you have fevers. Your healthcare provider will treat you as needed for your fever and any signs and symptoms of infection and should check your kidney function during and after you have had severe fever.
- serious skin reactions. Skin rash is a common side effect of TAFINLAR. TAFINLAR can also cause other skin reactions. In some cases, these rashes and other skin reactions can be severe or serious and may need to be treated in a hospital or lead to death.
  Tell your healthcare provider if you get a skin rash or acne that bothers you or worsens.
  Tell your healthcare provider right away if you develop any new or worsening symptoms of a severe skin reaction, including:

○ blisters or peeling of your skin
○ mouth sores

○ blisters on your lips, or around your mouth or eyes
○ high fever or flu-like symptoms
○ enlarged lymph nodes

- increased blood sugar (hyperglycemia). Some people may develop high blood sugar or worsening diabetes during treatment with TAFINLAR. If you are diabetic, your healthcare provider should check your blood sugar levels closely before and during treatment with TAFINLAR. Your diabetes medicine may need to be changed. Tell your healthcare provider if you have any of the following symptoms of severe high blood sugar:
  - increased thirst
  - urinating more often than normal, or urinating an increased amount of urine
- TAFINLAR may cause healthy red blood cells to break down too early in people with G6PD deficiency. This may lead to a type of anemia called hemolytic anemia where the body does not have enough healthy red blood cells. Tell your healthcare provider if you have any of the following signs or symptoms:
  ○ yellow skin (jaundice)
  ○ weakness or dizziness
  ○ shortness of breath

- hemophagocytic lymphohistiocytosis (HLH). TAFINLAR when taken or given with trametinib may increase the risk of a type of overactivity of the immune system (hemophagocytic lymphohistiocytosis) that can cause fever, swollen glands, bruising, or skin rash. If you experience a combination of these symptoms, call your healthcare provider right away.

The most common side effects of TAFINLAR when taken alone include:

• thickening of the outer layers of the skin

• warts

• headache

• hair loss

• fever

• redness, swelling, peeling, or tenderness of hands or feet

• joint aches

The most common side effects of TAFINLAR when taken with trametinib in people with melanoma that has spread to other parts of the body or cannot be removed by surgery include:

• fever

• headache

• rash

• joint aches

• chills

• cough

The most common side effects of TAFINLAR when taken with trametinib to help prevent melanoma from coming back after the cancer has been removed by surgery include:

• fever

• chills

• tiredness

• diarrhea

• nausea

• vomiting

• headache

• joint aches

• rash

• muscle aches

The most common side effects of TAFINLAR when taken with trametinib in people with NSCLC include:

• fever

• rash

• tiredness

• swelling of face, arms, and legs

• nausea

• chills

• vomiting

• bleeding

• diarrhea

• cough

• dry skin

• shortness of breath

• decreased appetite

The most common side effects of TAFINLAR when taken with trametinib in adults with solid tumors that cannot be removed by surgery or have spread to other parts of the body include:

• fever

• bleeding

• tiredness

• cough

• nausea

• vomiting

• rash

• constipation

• chills

• diarrhea

• headache

• muscle and joint aches

• swelling of your arms and legs

The most common side effects of TAFINLAR when taken or given with trametinib in children 1 year of age and older with solid tumors that cannot be removed by surgery or have spread to other parts of the body include:

• fever

• acne

• rash

• headache

• vomiting

• stomach-area (abdominal) pain

• tiredness

• nausea

• dry skin

• bleeding

• cough

• constipation

• diarrhea

• skin infection around fingernails or toenails

The most common side effects of TAFINLAR when taken or given with trametinib in children 1 year of age and older with low-grade glioma include:

• fever

• diarrhea

• rash

• dry skin

• headache

• nausea

• vomiting

• bleeding

• muscle and bone pain

• stomach-area (abdominal) pain

• tiredness

• acne

TAFINLAR may cause fertility problems in females. This could affect your ability to become pregnant. Talk to your healthcare provider if this is a concern for you.
TAFINLAR may cause lower sperm counts in males. This could affect the ability to father a child. Talk to your healthcare provider if this is a concern for you.
These are not all of the possible side effects of TAFINLAR.
Call your healthcare provider for medical advice about side effects. You may report side effects to FDA at 1-800-FDA-1088.
You may also report side effects to Novartis Pharmaceuticals Corporation at 1-888-669-6682.

How should I store TAFINLAR?
TAFINLAR Capsules:

- Store TAFINLAR capsules at room temperature between 68°F to 77°F (20°C to 25°C).
- Keep TAFINLAR capsules in the original bottle.
- The bottle of TAFINLAR capsules contains a canister with a drying agent (desiccant) to help keep your medicine dry. Do not throw away the desiccant canister.

TAFINLAR tablets for oral suspension:

- Store the bottle of TAFINLAR tablets for oral suspension at room temperature between 68°F to 77°F (20°C to 25°C).
- Store the bottle of TAFINLAR tablets for oral suspension, along with the two plastic canisters inside the original packaging, with the cap tightly closed. The canisters contain a drying agent (desiccant) to help keep your medicine dry.
- TAFINLAR tablets for oral suspension come in a bottle with a child-resistant cap.
- Throw away any TAFINLAR oral suspension if it is not taken or given within 30 minutes after it is prepared.

Keep TAFINLAR and all medicines out of the reach of children.

General information about the safe and effective use of TAFINLAR
Medicines are sometimes prescribed for purposes other than those listed in a Medication Guide. Do not use TAFINLAR for a condition for which it was not prescribed. Do not give TAFINLAR to other people, even if they have the same symptoms that you have. It may harm them. You can ask your healthcare provider or pharmacist for information about TAFINLAR that is written for health professionals.

What are the ingredients in TAFINLAR?
TAFINLAR Capsules:
Active ingredient: dabrafenib
Inactive ingredients: colloidal silicon dioxide, magnesium stearate, and microcrystalline cellulose.
Capsule shells: hypromellose, red iron oxide (E172), titanium dioxide (E171).
TAFINLAR Tablets for oral suspension:
Active ingredient: dabrafenib
Inactive ingredients: acesulfame potassium, artificial berry flavor, colloidal silicone dioxide, crospovidone, hypromellose, magnesium stearate, mannitol, microcrystalline cellulose.
Distributed by: Novartis Pharmaceuticals Corporation, East Hanover, New Jersey 07936
© Novartis
For more information, go to www.us.tafinlarmekinist.com or call 1-888-669-6682.

This Medication Guide has been approved by the U.S. Food and Drug Administration.

Revised: March 2025

T2025-23

INSTRUCTIONS FOR USE
TAFINLAR® (TAFF-in-lar)
(dabrafenib)
tablets for oral suspension

This “Instructions for Use” contains information on how to prepare and take or give TAFINLAR tablets for oral suspension.

Important information you need to know before taking or giving TAFINLAR tablets for oral suspension

- Read this “Instructions for Use” carefully before you prepare and take or give TAFINLAR oral suspension for the first time and each time you get a refill. There may be new information.
- This “Instructions for Use” does not take the place of talking with your healthcare provider about your or your child’s medical condition and treatment.
- Your healthcare provider or pharmacist should show you how to prepare and take or give a dose of TAFINLAR oral suspension correctly. Always take or give TAFINLAR exactly as your healthcare provider tells you to.
- If you have any questions about how to prepare and take or give a dose of TAFINLAR oral suspension, talk to your healthcare provider or pharmacist.
- Always use the dosing cup that comes with your TAFINLAR pack. If your pack does not contain a dosing cup, contact your healthcare provider or pharmacist.
- Use only clean water to rinse. Do not use soap or dishwashing liquid to clean the dosing cup.
- If at any time TAFINLAR oral suspension gets on your or your child’s skin, wash the area well with soap and water.
- If at any time TAFINLAR oral suspension gets in your or your child’s eyes, rinse the eyes well with cool water.
- If you spill any TAFINLAR oral suspension, follow the instructions at the end of this “Instructions for Use” in Section E. “How to clean up any spilled TAFINLAR oral suspension”.
- You will receive the TAFINLAR tablets in a sealed bottle. The TAFINLAR tablets must be mixed in water before taking or giving a dose of TAFINLAR oral suspension. The tablets break apart (disperse) in the water and may not fully dissolve. Follow the instructions below to mix the tablets in water.

The TAFINLAR pack should contain:

You will also need drinking water.
For taking or giving a dose of the TAFINLAR oral suspension by swallowing, go to Section A. For taking or giving a dose of the TAFINLAR oral suspension through a feeding tube or using an oral syringe, go to Section B.

Section A. Preparing and taking or giving a dose of the TAFINLAR oral suspension by swallowing directly from the dosing cup

If any of the TAFINLAR oral suspension comes into contact with your skin or eyes when you are following the steps below, follow instructions in the section “Important information you need to know before taking or giving TAFINLAR tablets for oral suspension”.
To prepare and take or give a dose of TAFINLAR oral suspension, you will need:

- the prescribed number of tablets
- 1 dosing cup
- 1 teaspoon
- drinking water

To take or give a dose of TAFINLAR oral suspension by mouth (swallowing the TAFINLAR oral suspension), you or your child can drink it directly from the dosing cup.

Step 1. Wash and dry your hands before preparing TAFINLAR tablets as an oral suspension.

- Add cool drinking water up to the markings on the dosing cup, as follows:

Note: The amount of water does not need to be exact.

- If the prescribed dose is 1 to 4 tablets, you will need about 5 mL of water.
- If the prescribed dose is 5 to 15 tablets, you will need about 10 mL of water.

Step 2. Remove the bottle cap by pushing down and turning counter-clockwise in the direction of the arrow, as shown.

- Do not throw away (dispose of) the cap.
- If you are opening the bottle for the first time, remove the seal from the bottle.

Step 3. Count out the prescribed number of tablets into your hand.

- Add the prescribed number of tablets into the water in your dosing cup.

- The bottle contains 2 plastic canisters to keep the tablets dry. If either canister falls out when you are taking out the tablets, re-insert it back into the bottle.

Step 4. Place the cap back onto the bottle and turn it clockwise in the direction of the arrow, as shown to close it.

Step 5. With one hand, tilt the dosing cup.

- With your other hand, gently stir the water and tablets with the handle of a teaspoon until the tablets break apart (disperse).
- It may take 3 minutes or more for the tablets to disperse. After the tablets disperse, the TAFINLAR oral suspension should be cloudy white, but may contain small pieces.
- Take or give the TAFINLAR oral suspension no later than 30 minutes after the tablets have been dispersed in water.
- If more than 30 minutes have passed, throw away the TAFINLAR oral suspension following the instructions in Section D and restart from the beginning of Section A. If you are not sure how to throw away the TAFINLAR oral suspension, ask your healthcare provider or pharmacist.

Step 6. Drink the TAFINLAR oral suspension from the dosing cup.
Important: After swallowing, there will be some medicine residue still inside the dosing cup. The medicine residue may be difficult to see. Follow Steps 7 through 9 to take or give any medicine residue still in the dosing cup so that you give the full dose of TAFINLAR.

Step 7. Add about 5 mL of water to the empty dosing cup.

Step 8. Stir with the handle of a teaspoon to loosen the remaining medicine residue.

Step 9. Drink the water and medicine residue mixture.

- If the prescribed dose is 1 to 4 tablets: Do Steps 7 through 9 one time.
- If the prescribed dose is 5 to 15 tablets: Do Steps 7 through 9 two times.

It is important to take or give all of the medicine residue so that you get the full dose of TAFINLAR.

Step 10. Go to Section C. “Cleaning the dosing cup and oral syringe (if used)”.

Section B. Preparing and giving TAFINLAR tablets as an oral suspension via feeding tube or oral syringe

Important administration information
Make sure all the tablets are dispersed before taking or giving the TAFINLAR oral suspension.
The minimum feeding tube size you may use to give the TAFINLAR oral suspension:

- If the prescribed dose is 1 to 3 tablets, the feeding tube size that may be used is 10 French gauge or larger.
- If the prescribed dose is 4 to 15 tablets, the feeding tube size that may be used is 12 French gauge or larger.
- If any of the TAFINLAR oral suspension comes into contact with your skin or eyes when you are following the steps below, follow the instructions in the section “Important information you need to know before taking or giving TAFINLAR tablets for oral suspension”.
- If any of the TAFINLAR oral suspension spills, follow the instruction in Section E. “How to clean up any spilled TAFINLAR oral suspension”.
- Wash and dry your hands before giving a dose of TAFINLAR oral suspension.

Step 1. Follow Steps 1 through 5 in Section A to disperse the TAFINLAR tablets. If using a feeding tube, flush the feeding tube with drinking water then continue with Step 2 below.

Step 2. Draw up all of the TAFINLAR oral suspension from the dosing cup into an oral syringe by pulling back on the plunger. Be sure to use an oral syringe that can be used with the feeding tube or that can be used to give the TAFINLAR oral suspension by mouth. Ask your healthcare provider if you are not sure what oral syringe to use.

Step 3. If giving the dose through a feeding tube, give the TAFINLAR oral suspension into the feeding tube according to the feeding tube manufacturer’s instructions.
If giving a dose of TAFINLAR oral suspension using an oral syringe, place the open end of the oral syringe inside the mouth with the tip pointing toward the inside of either cheek. If you are giving a dose of the TAFINLAR oral suspension to a child, make sure they are sitting upright.
Slowly push the plunger all the way down to give the full dose of TAFINLAR oral suspension.
Warning: Giving TAFINLAR oral suspension directly into the throat or pushing down on the plunger too fast may cause choking.

Step 4. Add about 5 mL of water to the empty dosing cup.

Step 5. Stir with the handle of a teaspoon to loosen the remaining medicine residue inside the dosing cup.

Step 6. Draw up the water and medicine residue mixture.

Step 7. Give the water and medicine residue mixture through the feeding tube or into the inside of the cheek.

- It is important to give all of the medicine residue that is left in the oral syringe and feeding tube. Repeat Steps 4 through 7 three times to make sure that you give a full dose of TAFINLAR.

Step 8. After repeating Steps 4 through 7 three times, flush the feeding tube with drinking water. Then go to the cleaning steps in Section C.

Section C. Cleaning the dosing cup and oral syringe (if used)

Use only clean water to rinse the dosing cup. Do not use soap or dishwashing liquid when cleaning the dosing cup.

Step 1. Rinse the dosing cup under clean cool water right away after dosing.

- Shake off excess water then wipe dry using clean paper towels.

Note: Keep the dosing cup away from other kitchen items.

Step 2. Rinse the teaspoon in clean cold water then wash in warm soapy water and dry using clean paper towels.

- You can also wash the teaspoon in a dishwasher.

Step 3. Clean the used oral syringe, as instructed by your healthcare provider, or according to the manufacturer’s instructions.

Section D. How to throw away TAFINLAR tablets or oral suspension that are expired or no longer needed, or old dosing cups

- Throw away unused TAFINLAR tablets or oral suspension, or old dosing cups into the trash. Do not pour TAFINLAR oral suspension down the drain.
- Ask your healthcare provider or pharmacist about how to safely throw away TAFINLAR tablets or oral suspension if you are not sure.

Section E. How to clean up any spilled TAFINLAR oral suspension

If you accidentally spill any TAFINLAR oral suspension, clean up the spill as follows:
1. Put on plastic gloves.
2. Soak up the spilled TAFINLAR oral suspension completely using an absorbent material, such as paper towels soaked with either a mixture of water and household disinfectant or with ethanol 70% (or higher grade).
3. Repeat the cleaning with fresh soaked absorbent material at least three times until the area is clean.
4. Dry the area with paper towels.
5. Throw away all the disposable materials used to clean the spillage into a sealable plastic bag.
6. Throw away the bags into the trash.
7. Wash your hands well with soap and water.

How should I store TAFINLAR tablets for oral suspension?

- Store the bottle of TAFINLAR tablets for oral suspension at room temperature between 68°F to 77°F (20°C to 25°C).
- Store the bottle of TAFINLAR tablets for oral suspension, along with the two plastic canisters inside the original packaging, with the cap tightly closed. The canisters contain a drying agent (desiccant) to help keep your medicine dry.
- TAFINLAR tablets for oral suspension come in a bottle with a child-resistant cap.
- Throw away any TAFINLAR oral suspension if it is not taken or given within 30 minutes after it is prepared.

Keep TAFINLAR and all medicines out of the reach of children.

Distributed by:
Novartis Pharmaceuticals Corporation
East Hanover, New Jersey 07936
© Novartis

This Instructions for Use has been approved by the U.S. Food and Drug Administration.

Revised: March 2024

T2024-24

PRINCIPAL DISPLAY PANEL

NDC 0078-0682-66

Tafinlar®
(Dabrafenib) Capsules

50 mg

Rx only

120 Capsules

Dispense with Medication Guide attached or provided separately.

NOVARTIS

PRINCIPAL DISPLAY PANEL

NDC 0078-0681-66

Tafinlar®
(Dabrafenib) Capsules

75 mg

Rx only

120 Capsules

Dispense with Medication Guide attached or provided separately.

NOVARTIS

PRINCIPAL DISPLAY PANEL

NDC 0078-1154-21

Rx only

Tafinlar®
(dabrafenib)

Tablets for Oral Suspension*

10 mg per tablet

*DISPERSE TABLETS IN WATER PRIOR TO INGESTION.

DO NOT SWALLOW WHOLE, CHEW OR CRUSH.

Dispense and store in original container with the desiccant**.

Dispense with Medication Guide.

210 Tablets

NOVARTIS